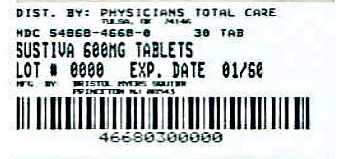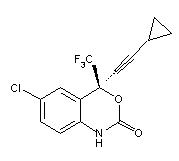 DRUG LABEL: SUSTIVA
NDC: 54868-4668 | Form: TABLET, FILM COATED
Manufacturer: Physicians Total Care, Inc.
Category: prescription | Type: HUMAN PRESCRIPTION DRUG LABEL
Date: 20130102

ACTIVE INGREDIENTS: efavirenz 600 mg/1 1
INACTIVE INGREDIENTS: croscarmellose sodium; hydroxypropyl cellulose; lactose monohydrate; magnesium stearate; cellulose, microcrystalline; sodium lauryl sulfate; carnauba wax

HIGHLIGHTS OF PRESCRIBING INFORMATION

These highlights do not include all the information needed to use SUSTIVA safely and effectively. See full prescribing information for SUSTIVA.
SUSTIVA® (efavirenz) capsules for oral use
SUSTIVA® (efavirenz) tablets for oral use
Initial U.S. Approval: 1998

RECENT MAJOR CHANGES

Dosage and Administration, Adults (2.1) 12/2011

Warnings and Precautions
Coadministration with Related Products (5.3) 08/2012
Rash (5.7) 06/2012
Immune Reconstitution Syndrome (5.11) 08/2012

1 INDICATIONS AND USAGE

SUSTIVA is a non-nucleoside reverse transcriptase inhibitor indicated in combination with other antiretroviral agents for the treatment of human immunodeficiency virus type 1 infection. (1)

2 DOSAGE AND ADMINISTRATION

- SUSTIVA should be taken orally once daily on an empty stomach, preferably at bedtime. (2)
- Recommended adult dose: 600 mg. (2.1)
- With voriconazole, increase voriconazole maintenance dose to 400 mg every 12 hours and decrease SUSTIVA dose to 300 mg once daily using the capsule formulation. (2.1)
- With rifampin, increase SUSTIVA dose to 800 mg once daily for patients weighing 50 kg or more. (2.1)

Pediatric Patients at Least 3 Years and at Least 10 kg (2.2)
kg | lbs | dose |  | kg | lbs | dose
10 - <15 | 22 - <33 | 200 mg |  | 25 - <32.5 | 55 - <71.5 | 350 mg
15 - <20 | 33 - <44 | 250 mg |  | 32.5 - <40 | 71.5 - <88 | 400 mg
20 - <25 | 44 - <55 | 300 mg |  | at least 40 | at least 88 | 600 mg

3 DOSAGE FORMS AND STRENGTHS

- Capsules: 200 mg and 50 mg. (3)
- Tablets: 600 mg. (3)

4 CONTRAINDICATIONS

- SUSTIVA is contraindicated in patients with previously demonstrated hypersensitivity (eg, Stevens-Johnson syndrome, erythema multiforme, or toxic skin eruptions) to any of the components of this product. (4.1)
- For some drugs, competition for CYP3A by efavirenz could result in inhibition of their metabolism and create the potential for serious and/or life-threatening adverse reactions (eg, cardiac arrhythmias, prolonged sedation, or respiratory depression). (4.2)

5 WARNINGS AND PRECAUTIONS

- Do not use as a single agent or add on as a sole agent to a failing regimen. Consider potential for cross resistance when choosing other agents. (5.2)
- Not recommended with ATRIPLA, which contains efavirenz, emtricitabine, and tenofovir disoproxil fumarate, unless needed for dose adjustment when coadministered with rifampin. (5.3)
- Serious psychiatric symptoms: Immediate medical evaluation is recommended for serious psychiatric symptoms such as severe depression or suicidal ideation. (5.4, 17.5)
- Nervous system symptoms (NSS): NSS are frequent, usually begin 1-2 days after initiating therapy and resolve in 2-4 weeks. Dosing at bedtime may improve tolerability. NSS are not predictive of onset of psychiatric symptoms. (5.5, 6.1, 17.4)
- Pregnancy: Fetal harm can occur when administered to a pregnant woman during the first trimester. Women should be apprised of the potential harm to the fetus. (5.6, 17.7) Pregnancy registry is available. (8.1)
- Hepatotoxicity: Monitor liver function tests before and during treatment in patients with underlying hepatic disease, including hepatitis B or C coinfection, marked transaminase elevations, or who are taking medications associated with liver toxicity. Among reported cases of hepatic failure, a few occurred in patients with no pre-existing hepatic disease. (5.8, 6.1, 8.6)
- Rash: Rash usually begins within 1-2 weeks after initiating therapy and resolves within 4 weeks. Discontinue if severe rash develops. (5.7, 6.1, 17.6)
- Convulsions: Use caution in patients with a history of seizures. (5.9)
- Lipids: Total cholesterol and triglyceride elevations. Monitor before therapy and periodically thereafter. (5.10)
- Immune reconstitution syndrome: May necessitate further evaluation and treatment. (5.11)
- Redistribution/accumulation of body fat: Observed in patients receiving antiretroviral therapy. (5.12, 17.8)

6 ADVERSE REACTIONS

Most common adverse reactions (>5%, moderate-severe) are rash, dizziness, nausea, headache, fatigue, insomnia, and vomiting. (6)

To report SUSPECTED ADVERSE REACTIONS, contact Bristol-Myers Squibb at 1-800-721-5072 or FDA at 1-800-FDA-1088 or www.fda.gov/medwatch.

7 DRUG INTERACTIONS

Coadministration of efavirenz can alter the concentrations of other drugs and other drugs may alter the concentrations of efavirenz. The potential for drug-drug interactions must be considered before and during therapy. (4.2, 7.1, 12.3)

8 USE IN SPECIFIC POPULATIONS

- Pregnancy: Women should avoid pregnancy during SUSTIVA therapy and for 12 weeks after discontinuation. (5.6)
- Nursing mothers: Women infected with HIV should be instructed not to breast-feed. (8.3)
- Hepatic impairment: SUSTIVA is not recommended for patients with moderate or severe hepatic impairment. Use caution in patients with mild hepatic impairment. (8.6)
- Pediatric patients: The incidence of rash was higher than in adults. (5.7, 6.1, 6.2, 8.4)

FULL PRESCRIBING INFORMATION

1 INDICATIONS AND USAGE

SUSTIVA® (efavirenz) in combination with other antiretroviral agents is indicated for the treatment of human immunodeficiency virus type 1 (HIV-1) infection. This indication is based on two clinical trials of at least one year duration that demonstrated prolonged suppression of HIV RNA [see Clinical Studies (14)].

2 DOSAGE AND ADMINISTRATION

2.1 Adults

The recommended dosage of SUSTIVA (efavirenz) is 600 mg orally, once daily, in combination with a protease inhibitor and/or nucleoside analogue reverse transcriptase inhibitors (NRTIs). It is recommended that SUSTIVA be taken on an empty stomach, preferably at bedtime. The increased efavirenz concentrations observed following administration of SUSTIVA with food may lead to an increase in frequency of adverse reactions [see Clinical Pharmacology (12.3)]. Dosing at bedtime may improve the tolerability of nervous system symptoms [see Warnings and Precautions (5.5), Adverse Reactions (6.1), and Patient Counseling Information (17.4)].

Concomitant Antiretroviral Therapy

SUSTIVA must be given in combination with other antiretroviral medications [see Indications and Usage (1), Warnings and Precautions (5.2), Drug Interactions (7.1), and Clinical Pharmacology (12.3)].

Dosage Adjustment

If SUSTIVA is coadministered with voriconazole, the voriconazole maintenance dose should be increased to 400 mg every 12 hours and the SUSTIVA dose should be decreased to 300 mg once daily using the capsule formulation (one 200-mg and two 50-mg capsules or six 50-mg capsules). SUSTIVA tablets should not be broken. See Drug Interactions (7.1, Table 7) and Clinical Pharmacology (12.3, Tables 8 and 9).

If SUSTIVA is coadministered with rifampin to patients weighing 50 kg or more, an increase in the dose of SUSTIVA to 800 mg once daily is recommended [see Drug Interactions (7.1, Table 7) and Clinical Pharmacology (12.3, Table 9)].

2.2 Pediatric Patients

It is recommended that SUSTIVA be taken on an empty stomach, preferably at bedtime. Table 1 describes the recommended dose of SUSTIVA for pediatric patients 3 years of age or older and weighing between 10 and 40 kg [see Use in Specific Populations (8.4)]. The recommended dosage of SUSTIVA for pediatric patients weighing greater than 40 kg is 600 mg once daily.

Table 1: Pediatric Dose to be Administered Once Daily
Body Weight |  | SUSTIVA Dose (mg)
kg | lbs | SUSTIVA Dose (mg)
10 to less than 15 | 22 to less than 33 | 200
15 to less than 20 | 33 to less than 44 | 250
20 to less than 25 | 44 to less than 55 | 300
25 to less than 32.5 | 55 to less than 71.5 | 350
32.5 to less than 40 | 71.5 to less than 88 | 400
at least 40 | at least 88 | 600

3 DOSAGE FORMS AND STRENGTHS

• Capsules

200-mg capsules are gold color, reverse printed with “SUSTIVA” on the body and imprinted “200 mg” on the cap.

50-mg capsules are gold color and white, printed with “SUSTIVA” on the gold color cap and reverse printed “50 mg” on the white body.

• Tablets

600-mg tablets are yellow, capsular-shaped, film-coated tablets, with “SUSTIVA” printed on both sides.

4 CONTRAINDICATIONS

4.1 Hypersensitivity

SUSTIVA is contraindicated in patients with previously demonstrated clinically significant hypersensitivity (eg, Stevens-Johnson syndrome, erythema multiforme, or toxic skin eruptions) to any of the components of this product.

4.2 Contraindicated Drugs

For some drugs, competition for CYP3A by efavirenz could result in inhibition of their metabolism and create the potential for serious and/or life-threatening adverse reactions (eg, cardiac arrhythmias, prolonged sedation, or respiratory depression). Drugs that are contraindicated with SUSTIVA are listed in Table 2.

Table 2: Drugs That Are Contraindicated or Not Recommended for Use With SUSTIVA
Drug Class: Drug Name | Clinical Comment
Antimigraine: ergot derivatives (dihydroergotamine, ergonovine, ergotamine, methylergonovine) | Potential for serious and/or life-threatening reactions such as acute ergot toxicity characterized by peripheral vasospasm and ischemia of the extremities and other tissues.
Benzodiazepines: midazolam, triazolam | Potential for serious and/or life-threatening reactions such as prolonged or increased sedation or respiratory depression.
Calcium channel blocker: bepridil | Potential for serious and/or life-threatening reactions such as cardiac arrhythmias.
GI motility agent: cisapride | Potential for serious and/or life-threatening reactions such as cardiac arrhythmias.
Neuroleptic: pimozide | Potential for serious and/or life-threatening reactions such as cardiac arrhythmias.
St. John’s wort (Hypericum perforatum) | May lead to loss of virologic response and possible resistance to efavirenz or to the class of non-nucleoside reverse transcriptase inhibitors (NNRTIs).

5 WARNINGS AND PRECAUTIONS

5.1 Drug Interactions

Efavirenz plasma concentrations may be altered by substrates, inhibitors, or inducers of CYP3A. Likewise, efavirenz may alter plasma concentrations of drugs metabolized by CYP3A or CYP2B6 [see Contraindications (4.2) and Drug Interactions (7.1)].

5.2 Resistance

SUSTIVA must not be used as a single agent to treat HIV-1 infection or added on as a sole agent to a failing regimen. Resistant virus emerges rapidly when efavirenz is administered as monotherapy. The choice of new antiretroviral agents to be used in combination with efavirenz should take into consideration the potential for viral cross-resistance.

5.3 Coadministration with Related Products

Coadministration of SUSTIVA with ATRIPLA (efavirenz 600 mg/emtricitabine 200 mg/tenofovir disoproxil fumarate 300 mg) is not recommended unless needed for dose adjustment (eg, with rifampin), since efavirenz is one of its active ingredients.

5.4 Psychiatric Symptoms

Serious psychiatric adverse experiences have been reported in patients treated with SUSTIVA. In controlled trials of 1008 patients treated with regimens containing SUSTIVA for a mean of 2.1 years and 635 patients treated with control regimens for a mean of 1.5 years, the frequency (regardless of causality) of specific serious psychiatric events among patients who received SUSTIVA or control regimens, respectively, were severe depression (2.4%, 0.9%), suicidal ideation (0.7%, 0.3%), nonfatal suicide attempts (0.5%, 0), aggressive behavior (0.4%, 0.5%), paranoid reactions (0.4%, 0.3%), and manic reactions (0.2%, 0.3%). When psychiatric symptoms similar to those noted above were combined and evaluated as a group in a multifactorial analysis of data from Study 006, treatment with efavirenz was associated with an increase in the occurrence of these selected psychiatric symptoms. Other factors associated with an increase in the occurrence of these psychiatric symptoms were history of injection drug use, psychiatric history, and receipt of psychiatric medication at study entry; similar associations were observed in both the SUSTIVA and control treatment groups. In Study 006, onset of new serious psychiatric symptoms occurred throughout the study for both SUSTIVA-treated and control-treated patients. One percent of SUSTIVA-treated patients discontinued or interrupted treatment because of one or more of these selected psychiatric symptoms. There have also been occasional postmarketing reports of death by suicide, delusions, and psychosis-like behavior, although a causal relationship to the use of SUSTIVA cannot be determined from these reports. Patients with serious psychiatric adverse experiences should seek immediate medical evaluation to assess the possibility that the symptoms may be related to the use of SUSTIVA, and if so, to determine whether the risks of continued therapy outweigh the benefits. See Adverse Reactions (6.1).

5.5 Nervous System Symptoms

Fifty-three percent (531/1008) of patients receiving SUSTIVA in controlled trials reported central nervous system symptoms (any grade, regardless of causality) compared to 25% (156/635) of patients receiving control regimens [see Adverse Reactions (6.1, Table 4)]. These symptoms included, but were not limited to, dizziness (28.1% of the 1008 patients), insomnia (16.3%), impaired concentration (8.3%), somnolence (7.0%), abnormal dreams (6.2%), and hallucinations (1.2%). These symptoms were severe in 2.0% of patients, and 2.1% of patients discontinued therapy as a result. These symptoms usually begin during the first or second day of therapy and generally resolve after the first 2-4 weeks of therapy. After 4 weeks of therapy, the prevalence of nervous system symptoms of at least moderate severity ranged from 5% to 9% in patients treated with regimens containing SUSTIVA and from 3% to 5% in patients treated with a control regimen. Patients should be informed that these common symptoms were likely to improve with continued therapy and were not predictive of subsequent onset of the less frequent psychiatric symptoms [see Warnings and Precautions (5.4)]. Dosing at bedtime may improve the tolerability of these nervous system symptoms [see Dosage and Administration (2)].

Analysis of long-term data from Study 006 (median follow-up 180 weeks, 102 weeks, and 76 weeks for patients treated with SUSTIVA + zidovudine + lamivudine, SUSTIVA + indinavir, and indinavir + zidovudine + lamivudine, respectively) showed that, beyond 24 weeks of therapy, the incidences of new-onset nervous system symptoms among SUSTIVA-treated patients were generally similar to those in the indinavir-containing control arm.

Patients receiving SUSTIVA should be alerted to the potential for additive central nervous system effects when SUSTIVA is used concomitantly with alcohol or psychoactive drugs.

Patients who experience central nervous system symptoms such as dizziness, impaired concentration, and/or drowsiness should avoid potentially hazardous tasks such as driving or operating machinery.

5.6 Reproductive Risk Potential

Pregnancy Category D. Efavirenz may cause fetal harm when administered during the first trimester to a pregnant woman. Pregnancy should be avoided in women receiving SUSTIVA. Barrier contraception must always be used in combination with other methods of contraception (eg, oral or other hormonal contraceptives). Because of the long half-life of efavirenz, use of adequate contraceptive measures for 12 weeks after discontinuation of SUSTIVA is recommended. Women of childbearing potential should undergo pregnancy testing before initiation of SUSTIVA. If this drug is used during the first trimester of pregnancy, or if the patient becomes pregnant while taking this drug, the patient should be apprised of the potential harm to the fetus.

There are no adequate and well-controlled studies in pregnant women. SUSTIVA should be used during pregnancy only if the potential benefit justifies the potential risk to the fetus, such as in pregnant women without other therapeutic options. [See Use in Specific Populations (8.1).]

5.7 Rash

In controlled clinical trials, 26% (266/1008) of patients treated with 600 mg SUSTIVA experienced new-onset skin rash compared with 17% (111/635) of patients treated in control groups [see Adverse Reactions (6.1, Table 5)]. Rash associated with blistering, moist desquamation, or ulceration occurred in 0.9% (9/1008) of patients treated with SUSTIVA. The incidence of Grade 4 rash (eg, erythema multiforme, Stevens-Johnson syndrome) in patients treated with SUSTIVA in all studies and expanded access was 0.1%. Rashes are usually mild-to-moderate maculopapular skin eruptions that occur within the first 2 weeks of initiating therapy with efavirenz (median time to onset of rash in adults was 11 days) and, in most patients continuing therapy with efavirenz, rash resolves within 1 month (median duration, 16 days). The discontinuation rate for rash in clinical trials was 1.7% (17/1008). SUSTIVA can be reinitiated in patients interrupting therapy because of rash. SUSTIVA should be discontinued in patients developing severe rash associated with blistering, desquamation, mucosal involvement, or fever. Appropriate antihistamines and/or corticosteroids may improve the tolerability and hasten the resolution of rash. For patients who have had a life-threatening cutaneous reaction (eg, Stevens-Johnson syndrome), alternative therapy should be considered [see also Contraindications (4.1)].

Rash was reported in 26 of 57 pediatric patients (46%) treated with SUSTIVA capsules [see Adverse Reactions (6.1, 6.2)]. One pediatric patient experienced Grade 3 rash (confluent rash with fever), and two patients had Grade 4 rash (erythema multiforme). The median time to onset of rash in pediatric patients was 8 days. Prophylaxis with appropriate antihistamines before initiating therapy with SUSTIVA in pediatric patients should be considered.

5.8 Hepatotoxicity

Monitoring of liver enzymes before and during treatment is recommended for patients with underlying hepatic disease, including hepatitis B or C infection; patients with marked transaminase elevations; and patients treated with other medications associated with liver toxicity [see Adverse Reactions (6.1) and Use in Specific Populations (8.6)]. A few of the postmarketing reports of hepatic failure occurred in patients with no pre-existing hepatic disease or other identifiable risk factors [see Adverse Reactions (6.3)]. Liver enzyme monitoring should also be considered for patients without pre-existing hepatic dysfunction or other risk factors. In patients with persistent elevations of serum transaminases to greater than five times the upper limit of the normal range, the benefit of continued therapy with SUSTIVA needs to be weighed against the unknown risks of significant liver toxicity.

5.9 Convulsions

Convulsions have been observed in patients receiving efavirenz, generally in the presence of known medical history of seizures [see Nonclinical Toxicology (13.2)]. Caution must be taken in any patient with a history of seizures. Patients who are receiving concomitant anticonvulsant medications primarily metabolized by the liver, such as phenytoin and phenobarbital, may require periodic monitoring of plasma levels [see Drug Interactions (7.1)].

5.10 Lipid Elevations

Treatment with SUSTIVA has resulted in increases in the concentration of total cholesterol and triglycerides [see Adverse Reactions (6.1)]. Cholesterol and triglyceride testing should be performed before initiating SUSTIVA therapy and at periodic intervals during therapy.

5.11 Immune Reconstitution Syndrome

Immune reconstitution syndrome has been reported in patients treated with combination antiretroviral therapy, including SUSTIVA. During the initial phase of combination antiretroviral treatment, patients whose immune system responds may develop an inflammatory response to indolent or residual opportunistic infections [such as Mycobacterium avium infection, cytomegalovirus, Pneumocystis jiroveci pneumonia (PCP), or tuberculosis], which may necessitate further evaluation and treatment.

Autoimmune disorders (such as Graves’ disease, polymyositis, and Guillain-Barré syndrome) have also been reported to occur in the setting of immune reconstitution; however, the time to onset is more variable, and can occur many months after initiation of treatment.

5.12 Fat Redistribution

Redistribution/accumulation of body fat including central obesity, dorsocervical fat enlargement (buffalo hump), peripheral wasting, facial wasting, breast enlargement, and “cushingoid appearance” have been observed in patients receiving antiretroviral therapy. The mechanism and long-term consequences of these events are currently unknown. A causal relationship has not been established.

6 ADVERSE REACTIONS

The most significant adverse reactions observed in patients treated with SUSTIVA are:

- psychiatric symptoms [see Warnings and Precautions (5.4)],
- nervous system symptoms [see Warnings and Precautions (5.5)],
- rash [see Warnings and Precautions (5.7)].

The most common (>5% in either efavirenz treatment group) adverse reactions of at least moderate severity among patients in Study 006 treated with SUSTIVA in combination with zidovudine/lamivudine or indinavir were rash, dizziness, nausea, headache, fatigue, insomnia, and vomiting.

6.1 Clinical Trials Experience in Adults

Because clinical studies are conducted under widely varying conditions, the adverse reaction rates reported cannot be directly compared to rates in other clinical studies and may not reflect the rates observed in clinical practice.

Selected clinical adverse reactions of moderate or severe intensity observed in ≥2% of SUSTIVA-treated patients in two controlled clinical trials are presented in Table 3.

Table 3: Selected Treatment-Emergenta Adverse Reactions of Moderate or Severe Intensity Reported in ≥2% of SUSTIVA-Treated Patients in Studies 006 and ACTG 364
 | Study 006 LAM-, NNRTI-, and Protease Inhibitor-Naive Patients |  |  | Study ACTG 364 NRTI-experienced, NNRTI-, and Protease Inhibitor-Naive Patients
Adverse Reactions | SUSTIVAb + ZDV/LAM (n=412) | SUSTIVAb + Indinavir (n=415) | Indinavir + ZDV/LAM (n=401) | SUSTIVAb + Nelfinavir + NRTIs (n=64) | SUSTIVAb + NRTIs (n=65) | Nelfinavir + NRTIs (n=66)
Adverse Reactions | 180 weeksc | 102 weeksc | 76 weeksc | 71.1 weeksc | 70.9 weeksc | 62.7 weeksc
Body as a Whole
Fatigue | 8% | 5% | 9% | 0 | 2% | 3%
Pain | 1% | 2% | 8% | 13% | 6% | 17%
Central and Peripheral Nervous System
Dizziness | 9% | 9% | 2% | 2% | 6% | 6%
Headache | 8% | 5% | 3% | 5% | 2% | 3%
Insomnia | 7% | 7% | 2% | 0 | 0 | 2%
Concentration impaired | 5% | 3% | <1% | 0 | 0 | 0
Abnormal dreams | 3% | 1% | 0 | — | — | —
Somnolence | 2% | 2% | <1% | 0 | 0 | 0
Anorexia | 1% | <1% | <1% | 0 | 2% | 2%
Gastrointestinal
Nausea | 10% | 6% | 24% | 3% | 2% | 2%
Vomiting | 6% | 3% | 14% | — | — | —
Diarrhea | 3% | 5% | 6% | 14% | 3% | 9%
Dyspepsia | 4% | 4% | 6% | 0 | 0 | 2%
Abdominal pain | 2% | 2% | 5% | 3% | 3% | 3%
Psychiatric
Anxiety | 2% | 4% | <1% | — | — | —
Depression | 5% | 4% | <1% | 3% | 0 | 5%
Nervousness | 2% | 2% | 0 | 2% | 0 | 2%
Skin & Appendages
Rashd | 11% | 16% | 5% | 9% | 5% | 9%
Pruritus | <1% | 1% | 1% | 9% | 5% | 9%
a Includes adverse events at least possibly related to study drug or of unknown relationship for Study 006. Includes all adverse events regardless of relationship to study drug for Study ACTG 364.
b SUSTIVA provided as 600 mg once daily.
c Median duration of treatment.
d Includes erythema multiforme, rash, rash erythematous, rash follicular, rash maculopapular, rash petechial, rash pustular, and urticaria for Study 006 and macules, papules, rash, erythema, redness, inflammation, allergic rash, urticaria, welts, hives, itchy, and pruritus for ACTG 364.
— = Not Specified.
ZDV = zidovudine, LAM = lamivudine.

Pancreatitis has been reported, although a causal relationship with efavirenz has not been established. Asymptomatic increases in serum amylase levels were observed in a significantly higher number of patients treated with efavirenz 600 mg than in control patients (see Laboratory Abnormalities).

Nervous System Symptoms

For 1008 patients treated with regimens containing SUSTIVA and 635 patients treated with a control regimen in controlled trials, Table 4 lists the frequency of symptoms of different degrees of severity and gives the discontinuation rates for one or more of the following nervous system symptoms: dizziness, insomnia, impaired concentration, somnolence, abnormal dreaming, euphoria, confusion, agitation, amnesia, hallucinations, stupor, abnormal thinking, and depersonalization [see Warnings and Precautions (5.5)]. The frequencies of specific central and peripheral nervous system symptoms are provided in Table 3.

Table 4: Percent of Patients with One or More Selected Nervous System Symptomsa,b
Percent of Patients with: | SUSTIVA 600 mg Once Daily (n=1008) | Control Groups (n=635)
Percent of Patients with: | % | %
Symptoms of any severity | 52.7 | 24.6
Mild symptomsc | 33.3 | 15.6
Moderate symptomsd | 17.4 | 7.7
Severe symptomse | 2.0 | 1.3
Treatment discontinuation as a result of symptoms | 2.1 | 1.1
a Includes events reported regardless of causality.
b Data from Study 006 and three Phase 2/3 studies.
c “Mild” = Symptoms which do not interfere with patient’s daily activities.
d “Moderate” = Symptoms which may interfere with daily activities.
e “Severe” = Events which interrupt patient’s usual daily activities.

Psychiatric Symptoms

Serious psychiatric adverse experiences have been reported in patients treated with SUSTIVA. In controlled trials, psychiatric symptoms observed at a frequency of >2% among patients treated with SUSTIVA or control regimens, respectively, were depression (19%, 16%), anxiety (13%, 9%), and nervousness (7%, 2%).

Rash

For 1008 adult and 57 pediatric patients treated with regimens containing SUSTIVA and 635 patients treated with a control regimen in controlled trials, the frequency of rash by NCI grade and the discontinuation rates as a result of rash in clinical studies are provided in Table 5 [see Warnings and Precautions (5.7)].

Table 5: Percent of Patients with Treatment-Emergent Rasha,b
Percent of Patients with: | Description of Rash Gradec | SUSTIVA 600 mg Once Daily Adults (n=1008) | SUSTIVA Pediatric Patients (n=57) | Control Groups Adults (n=635)
Percent of Patients with: | Description of Rash Gradec | % | % | %
Rash of any grade | — | 26.3 | 45.6 | 17.5
Grade 1 rash | Erythema, pruritus | 10.7 | 8.8 | 9.8
Grade 2 rash | Diffuse maculopapular rash, dry desquamation | 14.7 | 31.6 | 7.4
Grade 3 rash | Vesiculation, moist desquamation, ulceration | 0.8 | 1.8 | 0.3
Grade 4 rash | Erythema multiforme, Stevens-Johnson syndrome, toxic epidermal necrolysis, necrosis requiring surgery, exfoliative dermatitis | 0.1 | 3.5 | 0.0
Treatment discontinuation as a result of rash | — | 1.7 | 8.8 | 0.3
a Includes events reported regardless of causality.
b Data from Study 006 and three Phase 2/3 studies.
c NCI Grading System.

As seen in Table 5, rash is more common in pediatric patients and more often of higher grade (ie, more severe) [see Warnings and Precautions (5.7)].

Experience with SUSTIVA in patients who discontinued other antiretroviral agents of the NNRTI class is limited. Nineteen patients who discontinued nevirapine because of rash have been treated with SUSTIVA. Nine of these patients developed mild-to-moderate rash while receiving therapy with SUSTIVA, and two of these patients discontinued because of rash.

Laboratory Abnormalities

Selected Grade 3-4 laboratory abnormalities reported in ≥2% of SUSTIVA-treated patients in two clinical trials are presented in Table 6.

Table 6: Selected Grade 3-4 Laboratory Abnormalities Reported in ≥2% of SUSTIVA-Treated Patients in Studies 006 and ACTG 364
 |  | Study 006 LAM-, NNRTI-, and Protease Inhibitor-Naive Patients |  |  | Study ACTG 364 NRTI-experienced, NNRTI-, and Protease Inhibitor-Naive Patients
Variable | Limit | SUSTIVAa + ZDV/LAM (n=412) | SUSTIVAa + Indinavir (n=415) | Indinavir + ZDV/LAM (n=401) | SUSTIVAa + Nelfinavir + NRTIs (n=64) | SUSTIVAa + NRTIs (n=65) | Nelfinavir + NRTIs (n=66)
Variable | Limit | 180 weeksb | 102 weeksb | 76 weeksb | 71.1 weeksb | 70.9 weeksb | 62.7 weeksb
Chemistry
ALT | >5 x ULN | 5% | 8% | 5% | 2% | 6% | 3%
AST | >5 x ULN | 5% | 6% | 5% | 6% | 8% | 8%
GGTc | >5 x ULN | 8% | 7% | 3% | 5% | 0 | 5%
Amylase | >2 x ULN | 4% | 4% | 1% | 0 | 6% | 2%
Glucose | >250 mg/dL | 3% | 3% | 3% | 5% | 2% | 3%
Triglyceridesd | ≥751 mg/dL | 9% | 6% | 6% | 11% | 8% | 17%
Hematology
Neutrophils | <750/mm^3 | 10% | 3% | 5% | 2% | 3% | 2%
a SUSTIVA provided as 600 mg once daily.
b Median duration of treatment.
c Isolated elevations of GGT in patients receiving SUSTIVA may reflect enzyme induction not associated with liver toxicity.
d Nonfasting.
ZDV = zidovudine, LAM = lamivudine, ULN = Upper limit of normal, ALT = alanine aminotransferase,
AST = aspartate aminotransferase, GGT = gamma-glutamyltransferase.

Patients Coinfected with Hepatitis B or C

Liver function tests should be monitored in patients with a history of hepatitis B and/or C. In the long-term data set from Study 006, 137 patients treated with SUSTIVA-containing regimens (median duration of therapy, 68 weeks) and 84 treated with a control regimen (median duration, 56 weeks) were seropositive at screening for hepatitis B (surface antigen positive) and/or C (hepatitis C antibody positive). Among these coinfected patients, elevations in AST to greater than five times ULN developed in 13% of patients in the SUSTIVA arms and 7% of those in the control arm, and elevations in ALT to greater than five times ULN developed in 20% of patients in the SUSTIVA arms and 7% of patients in the control arm. Among coinfected patients, 3% of those treated with SUSTIVA-containing regimens and 2% in the control arm discontinued from the study because of liver or biliary system disorders [see Warnings and Precautions (5.8)].

Lipids

Increases from baseline in total cholesterol of 10-20% have been observed in some uninfected volunteers receiving SUSTIVA. In patients treated with SUSTIVA + zidovudine + lamivudine, increases from baseline in nonfasting total cholesterol and HDL of approximately 20% and 25%, respectively, were observed. In patients treated with SUSTIVA + indinavir, increases from baseline in nonfasting cholesterol and HDL of approximately 40% and 35%, respectively, were observed. Nonfasting total cholesterol levels ≥240 mg/dL and ≥300 mg/dL were reported in 34% and 9%, respectively, of patients treated with SUSTIVA + zidovudine + lamivudine; 54% and 20%, respectively, of patients treated with SUSTIVA + indinavir; and 28% and 4%, respectively, of patients treated with indinavir + zidovudine + lamivudine. The effects of SUSTIVA on triglycerides and LDL in this study were not well characterized since samples were taken from nonfasting patients. The clinical significance of these findings is unknown [see Warnings and Precautions (5.10)].

6.2 Clinical Trial Experience in Pediatric Patients

Clinical adverse experiences observed in ≥10% of 57 pediatric patients aged 3 to 16 years who received SUSTIVA capsules, nelfinavir, and one or more NRTIs in Study ACTG 382 [see Use In Specific Populations (8.4)] were rash (46%), diarrhea/loose stools (39%), fever (21%), cough (16%), dizziness/lightheaded/fainting (16%), ache/pain/discomfort (14%), nausea/vomiting (12%), and headache (11%). The incidence of nervous system symptoms was 18% (10/57). One patient experienced Grade 3 rash, two patients had Grade 4 rash, and five patients (9%) discontinued because of rash [see Warnings and Precautions (5.7) and Adverse Reactions (6.1, Table 5)].

6.3 Postmarketing Experience

The following adverse reactions have been identified during postapproval use of SUSTIVA. Because these reactions are reported voluntarily from a population of unknown size, it is not always possible to reliably estimate their frequency or establish a causal relationship to drug exposure.

Body as a Whole: allergic reactions, asthenia, redistribution/accumulation of body fat [see Warnings and Precautions (5.12)]

Central and Peripheral Nervous System: abnormal coordination, ataxia, cerebellar coordination and balance disturbances, convulsions, hypoesthesia, paresthesia, neuropathy, tremor, vertigo

Endocrine: gynecomastia

Gastrointestinal: constipation, malabsorption

Cardiovascular: flushing, palpitations

Liver and Biliary System: hepatic enzyme increase, hepatic failure, hepatitis. A few of the postmarketing reports of hepatic failure, including cases in patients with no pre-existing hepatic disease or other identifiable risk factors, were characterized by a fulminant course, progressing in some cases to transplantation or death.

Metabolic and Nutritional: hypercholesterolemia, hypertriglyceridemia

Musculoskeletal: arthralgia, myalgia, myopathy

Psychiatric: aggressive reactions, agitation, delusions, emotional lability, mania, neurosis, paranoia, psychosis, suicide

Respiratory: dyspnea

Skin and Appendages: erythema multiforme, photoallergic dermatitis, Stevens-Johnson syndrome

Special Senses: abnormal vision, tinnitus

7 DRUG INTERACTIONS

7.1 Drug-Drug Interactions

Efavirenz has been shown in vivo to induce CYP3A and CYP2B6. Other compounds that are substrates of CYP3A or CYP2B6 may have decreased plasma concentrations when coadministered with SUSTIVA. In vitro studies have demonstrated that efavirenz inhibits CYP2C9, 2C19, and 3A4 isozymes in the range of observed efavirenz plasma concentrations. Coadministration of efavirenz with drugs primarily metabolized by these isozymes may result in altered plasma concentrations of the coadministered drug. Therefore, appropriate dose adjustments may be necessary for these drugs.

Drugs that induce CYP3A activity (eg, phenobarbital, rifampin, rifabutin) would be expected to increase the clearance of efavirenz resulting in lowered plasma concentrations. Drug interactions with SUSTIVA are summarized in Tables 2 and 7 [for pharmacokinetics data see Clinical Pharmacology (12.3, Tables 8 and 9)]. The tables include potentially significant interactions, but are not all inclusive.

Table 7: Established and Other Potentially Significant Drug Interactions: Alteration in Dose or Regimen May Be Recommended Based on Drug Interaction Studies or Predicted Interaction
Concomitant Drug Class: Drug Name | Effect | Clinical Comment
HIV antiviral agents
Protease inhibitor: Fosamprenavir calcium | ↓ amprenavir | Fosamprenavir (unboosted): Appropriate doses of the combinations with respect to safety and efficacy have not been established. Fosamprenavir/ritonavir: An additional 100 mg/day (300 mg total) of ritonavir is recommended when SUSTIVA is administered with fosamprenavir/ritonavir once daily. No change in the ritonavir dose is required when SUSTIVA is administered with fosamprenavir plus ritonavir twice daily.
Protease inhibitor: Atazanavir sulfate | ↓ atazanavir* | Treatment-naive patients: When coadministered with SUSTIVA, the recommended dose of atazanavir is 400 mg with ritonavir 100 mg (together once daily with food) and SUSTIVA 600 mg (once daily on an empty stomach, preferably at bedtime). Treatment-experienced patients: Coadministration of SUSTIVA and atazanavir is not recommended.
Protease inhibitor: Indinavir | ↓ indinavir* | The optimal dose of indinavir, when given in combination with SUSTIVA, is not known. Increasing the indinavir dose to 1000 mg every 8 hours does not compensate for the increased indinavir metabolism due to SUSTIVA. When indinavir at an increased dose (1000 mg every 8 hours) was given with SUSTIVA (600 mg once daily), the indinavir AUC and Cmin were decreased on average by 33-46% and 39-57%, respectively, compared to when indinavir (800 mg every 8 hours) was given alone.
Protease inhibitor: Lopinavir/ritonavir | ↓ lopinavir* | Lopinavir/ritonavir tablets should not be administered once daily in combination with SUSTIVA. In antiretroviral-naive patients, lopinavir/ritonavir tablets can be used twice daily in combination with SUSTIVA with no dose adjustment. A dose increase of lopinavir/ritonavir tablets to 600/150 mg (3 tablets) twice daily may be considered when used in combination with SUSTIVA in treatment-experienced patients where decreased susceptibility to lopinavir is clinically suspected (by treatment history or laboratory evidence). A dose increase of lopinavir/ritonavir oral solution to 533/133 mg (6.5 mL) twice daily taken with food is recommended when used in combination with SUSTIVA.
Protease inhibitor: Ritonavir | ↑ ritonavir* ↑ efavirenz* | When ritonavir 500 mg q12h was coadministered with SUSTIVA 600 mg once daily, the combination was associated with a higher frequency of adverse clinical experiences (eg, dizziness, nausea, paresthesia) and laboratory abnormalities (elevated liver enzymes). Monitoring of liver enzymes is recommended when SUSTIVA is used in combination with ritonavir.
Protease inhibitor: Saquinavir | ↓ saquinavir* | Should not be used as sole protease inhibitor in combination with SUSTIVA.
NNRTI: Other NNRTIs | ↑ or ↓ efavirenz and/or NNRTI | Combining two NNRTIs has not been shown to be beneficial. SUSTIVA should not be coadministered with other NNRTIs.
CCR5 co-receptor antagonist: Maraviroc | ↓ maraviroc* | Refer to the full prescribing information for maraviroc for guidance on coadministration with efavirenz.
Integrase strand transfer inhibitor: Raltegravir | ↓ raltegravir* | SUSTIVA reduces plasma concentrations of raltegravir. The clinical significance of this interaction has not been directly assessed.
Hepatitis C antiviral agents
Protease inhibitor: Boceprevir | ↓ boceprevir* | Plasma trough concentrations of boceprevir were decreased when boceprevir was coadministered with SUSTIVA, which may result in loss of therapeutic effect. The combination should be avoided.
Protease inhibitor: Telaprevir | ↓ telaprevir* ↓ efavirenz* | Concomitant administration of telaprevir and SUSTIVA resulted in reduced steady-state exposures to telaprevir and efavirenz.
Other agents
Anticoagulant: Warfarin | ↑ or ↓ warfarin | Plasma concentrations and effects potentially increased or decreased by SUSTIVA.
Anticonvulsants: Carbamazepine | ↓ carbamazepine* ↓ efavirenz* | There are insufficient data to make a dose recommendation for efavirenz. Alternative anticonvulsant treatment should be used.
Phenytoin Phenobarbital | ↓ anticonvulsant ↓ efavirenz | Potential for reduction in anticonvulsant and/or efavirenz plasma levels; periodic monitoring of anticonvulsant plasma levels should be conducted.
Antidepressants: Bupropion | ↓ bupropion* | The effect of efavirenz on bupropion exposure is thought to be due to the induction of bupropion metabolism. Increases in bupropion dosage should be guided by clinical response, but the maximum recommended dose of bupropion should not be exceeded.
Sertraline | ↓ sertraline* | Increases in sertraline dosage should be guided by clinical response.
Antifungals: Voriconazole | ↓ voriconazole* ↑ efavirenz* | SUSTIVA and voriconazole must not be coadministered at standard doses. Efavirenz significantly decreases voriconazole plasma concentrations, and coadministration may decrease the therapeutic effectiveness of voriconazole. Also, voriconazole significantly increases efavirenz plasma concentrations, which may increase the risk of SUSTIVA-associated side effects. When voriconazole is coadministered with SUSTIVA, voriconazole maintenance dose should be increased to 400 mg every 12 hours and SUSTIVA dose should be decreased to 300 mg once daily using the capsule formulation. SUSTIVA tablets should not be broken. [See Dosage and Administration (2.1) and Clinical Pharmacology (12.3, Tables 8 and 9).]
Itraconazole | ↓ itraconazole* ↓ hydroxyitraconazole* | Since no dose recommendation for itraconazole can be made, alternative antifungal treatment should be considered.
Ketoconazole | ↓ ketoconazole | Drug interaction studies with SUSTIVA and ketoconazole have not been conducted. SUSTIVA has the potential to decrease plasma concentrations of ketoconazole.
Posaconazole | ↓ posaconazole* | Avoid concomitant use unless the benefit outweighs the risks.
Anti-infective: Clarithromycin | ↓ clarithromycin* ↑ 14-OH metabolite* | Plasma concentrations decreased by SUSTIVA; clinical significance unknown. In uninfected volunteers, 46% developed rash while receiving SUSTIVA and clarithromycin. No dose adjustment of SUSTIVA is recommended when given with clarithromycin. Alternatives to clarithromycin, such as azithromycin, should be considered (see Other Drugs, following table). Other macrolide antibiotics, such as erythromycin, have not been studied in combination with SUSTIVA.
Antimycobacterials: Rifabutin | ↓ rifabutin* | Increase daily dose of rifabutin by 50%. Consider doubling the rifabutin dose in regimens where rifabutin is given 2 or 3 times a week.
Rifampin | ↓ efavirenz* | If SUSTIVA is coadministered with rifampin to patients weighing 50 kg or more, an increase in the dose of SUSTIVA to 800 mg once daily is recommended.
Calcium channel blockers: Diltiazem | ↓ diltiazem* ↓ desacetyl diltiazem* ↓ N-monodesmethyl diltiazem* | Diltiazem dose adjustments should be guided by clinical response (refer to the full prescribing information for diltiazem). No dose adjustment of efavirenz is necessary when administered with diltiazem.
Others (eg, felodipine, nicardipine, nifedipine, verapamil) | ↓ calcium channel blocker | No data are available on the potential interactions of efavirenz with other calcium channel blockers that are substrates of CYP3A. The potential exists for reduction in plasma concentrations of the calcium channel blocker. Dose adjustments should be guided by clinical response (refer to the full prescribing information for the calcium channel blocker).
HMG-CoA reductase inhibitors: Atorvastatin Pravastatin Simvastatin | ↓ atorvastatin* ↓ pravastatin* ↓ simvastatin* | Plasma concentrations of atorvastatin, pravastatin, and simvastatin decreased. Consult the full prescribing information for the HMG-CoA reductase inhibitor for guidance on individualizing the dose.
Hormonal contraceptives: Oral Ethinyl estradiol/ Norgestimate | ↓ active metabolites of norgestimate* | A reliable method of barrier contraception must be used in addition to hormonal contraceptives. Efavirenz had no effect on ethinyl estradiol concentrations, but progestin levels (norelgestromin and levonorgestrel) were markedly decreased. No effect of ethinyl estradiol/norgestimate on efavirenz plasma concentrations was observed.
Implant Etonogestrel | ↓ etonogestrel | A reliable method of barrier contraception must be used in addition to hormonal contraceptives. The interaction between etonogestrel and efavirenz has not been studied. Decreased exposure of etonogestrel may be expected. There have been postmarketing reports of contraceptive failure with etonogestrel in efavirenz-exposed patients.
Immunosuppressants: Cyclosporine, tacrolimus, sirolimus, and others metabolized by CYP3A | ↓ immunosuppressant | Decreased exposure of the immunosuppressant may be expected due to CYP3A induction. These immunosuppressants are not anticipated to affect exposure of efavirenz. Dose adjustments of the immunosuppressant may be required. Close monitoring of immunosuppressant concentrations for at least 2 weeks (until stable concentrations are reached) is recommended when starting or stopping treatment with efavirenz.
Narcotic analgesic: Methadone | ↓ methadone* | Coadministration in HIV-infected individuals with a history of injection drug use resulted in decreased plasma levels of methadone and signs of opiate withdrawal. Methadone dose was increased by a mean of 22% to alleviate withdrawal symptoms. Patients should be monitored for signs of withdrawal and their methadone dose increased as required to alleviate withdrawal symptoms.
* The interaction between SUSTIVA and the drug was evaluated in a clinical study. All other drug interactions shown are predicted.
This table is not all-inclusive.

Other Drugs

Based on the results of drug interaction studies [see Clinical Pharmacology (12.3, Tables 8 and 9)], no dosage adjustment is recommended when SUSTIVA (efavirenz) is given with the following: aluminum/magnesium hydroxide antacids, azithromycin, cetirizine, famotidine, fluconazole, lamivudine, lorazepam, nelfinavir, paroxetine, tenofovir disoproxil fumarate, and zidovudine.

Specific drug interaction studies have not been performed with SUSTIVA and NRTIs other than lamivudine and zidovudine. Clinically significant interactions would not be expected since the NRTIs are metabolized via a different route than efavirenz and would be unlikely to compete for the same metabolic enzymes and elimination pathways.

7.2 Cannabinoid Test Interaction

Efavirenz does not bind to cannabinoid receptors. False-positive urine cannabinoid test results have been observed in non-HIV-infected volunteers receiving SUSTIVA when the Microgenics CEDIA DAU Multi-Level THC assay was used for screening. Negative results were obtained when more specific confirmatory testing was performed with gas chromatography/mass spectrometry.

Of the three assays analyzed (Microgenics CEDIA DAU Multi-Level THC assay, Cannabinoid Enzyme Immunoassay [Diagnostic Reagents, Inc], and AxSYM Cannabinoid Assay), only the Microgenics CEDIA DAU Multi-Level THC assay showed false-positive results. The other two assays provided true-negative results. The effects of SUSTIVA on cannabinoid screening tests other than these three are unknown. The manufacturers of cannabinoid assays should be contacted for additional information regarding the use of their assays with patients receiving efavirenz.

8 USE IN SPECIFIC POPULATIONS

8.1 Pregnancy

Pregnancy Category D: See Warnings and Precautions (5.6).

Antiretroviral Pregnancy Registry: To monitor fetal outcomes of pregnant women exposed to SUSTIVA, an Antiretroviral Pregnancy Registry has been established. Physicians are encouraged to register patients by calling 1-800-258-4263.

As of July 2010, the Antiretroviral Pregnancy Registry has received prospective reports of 792 pregnancies exposed to efavirenz-containing regimens, nearly all of which were first-trimester exposures (718 pregnancies). Birth defects occurred in 17 of 604 live births (first-trimester exposure) and 2 of 69 live births (second/third-trimester exposure). One of these prospectively reported defects with first-trimester exposure was a neural tube defect. A single case of anophthalmia with first-trimester exposure to efavirenz has also been prospectively reported; however, this case included severe oblique facial clefts and amniotic banding, a known association with anophthalmia. There have been six retrospective reports of findings consistent with neural tube defects, including meningomyelocele. All mothers were exposed to efavirenz-containing regimens in the first trimester. Although a causal relationship of these events to the use of SUSTIVA has not been established, similar defects have been observed in preclinical studies of efavirenz.

Animal Data

Effects of efavirenz on embryo-fetal development have been studied in three nonclinical species (cynomolgus monkeys, rats, and rabbits). In monkeys, efavirenz 60 mg/kg/day was administered to pregnant females throughout pregnancy (gestation days 20 through 150). The maternal systemic drug exposures (AUC) were 1.3 times the exposure in humans at the recommended clinical dose (600 mg/day), with fetal umbilical venous drug concentrations approximately 0.7 times the maternal values. Three fetuses of 20 fetuses/infants had one or more malformations; there were no malformed fetuses or infants from placebo-treated mothers. The malformations that occurred in these three monkey fetuses included anencephaly and unilateral anophthalmia in one fetus, microophthalmia in a second, and cleft palate in the third. There was no NOAEL (no observable adverse effect level) established for this study because only one dosage was evaluated. In rats, efavirenz was administered either during organogenesis (gestation days 7 to 18) or from gestation day 7 through lactation day 21 at 50, 100, or 200 mg/kg/day. Administration of 200 mg/kg/day in rats was associated with increase in the incidence of early resorptions; and doses 100 mg/kg/day and greater were associated with early neonatal mortality. The AUC at the NOAEL (50 mg/kg/day) in this rat study was 0.1 times that in humans at the recommended clinical dose. Drug concentrations in the milk on lactation day 10 were approximately 8 times higher than those in maternal plasma. In pregnant rabbits, efavirenz was neither embryo lethal nor teratogenic when administered at doses of 25, 50, and 75 mg/kg/day over the period of organogenesis (gestation days 6 through 18). The AUC at the NOAEL (75 mg/kg/day) in rabbits was 0.4 times that in humans at the recommended clinical dose.

8.3 Nursing Mothers

The Centers for Disease Control and Prevention recommend that HIV-infected mothers not breast-feed their infants to avoid risking postnatal transmission of HIV. Although it is not known if efavirenz is secreted in human milk, efavirenz is secreted into the milk of lactating rats. Because of the potential for HIV transmission and the potential for serious adverse effects in nursing infants, mothers should be instructed not to breast-feed if they are receiving SUSTIVA.

8.4 Pediatric Use

ACTG 382 is an ongoing, open-label study in 57 NRTI-experienced pediatric patients to characterize the safety, pharmacokinetics, and antiviral activity of SUSTIVA in combination with nelfinavir (20-30 mg/kg three times daily) and NRTIs. Mean age was 8 years (range 3-16). SUSTIVA has not been studied in pediatric patients below 3 years of age or who weigh less than 13 kg. At 48 weeks, the type and frequency of adverse experiences was generally similar to that of adult patients with the exception of a higher incidence of rash, which was reported in 46% (26/57) of pediatric patients compared to 26% of adults, and a higher frequency of Grade 3 or 4 rash reported in 5% (3/57) of pediatric patients compared to 0.9% of adults [see Warnings and Precautions (5.7) and Adverse Reactions (6.1, Table 5; 6.2)].

The starting dose of SUSTIVA was 600 mg once daily adjusted to body size, based on weight, targeting AUC levels in the range of 190-380 µM•h [see Dosage and Administration (2.2)]. The pharmacokinetics of efavirenz in pediatric patients were similar to the pharmacokinetics in adults who received 600-mg daily doses of SUSTIVA. In 48 pediatric patients receiving the equivalent of a 600-mg dose of SUSTIVA, steady-state Cmax was 14.2 ± 5.8 µM (mean ± SD), steady-state Cmin was 5.6 ± 4.1 µM, and AUC was 218 ± 104 µM•h.

8.5 Geriatric Use

Clinical studies of SUSTIVA did not include sufficient numbers of subjects aged 65 years and over to determine whether they respond differently from younger subjects. In general, dose selection for an elderly patient should be cautious, reflecting the greater frequency of decreased hepatic, renal, or cardiac function and of concomitant disease or other therapy.

8.6 Hepatic Impairment

SUSTIVA is not recommended for patients with moderate or severe hepatic impairment because there are insufficient data to determine whether dose adjustment is necessary. Patients with mild hepatic impairment may be treated with efavirenz without any adjustment in dose. Because of the extensive cytochrome P450-mediated metabolism of efavirenz and limited clinical experience in patients with hepatic impairment, caution should be exercised in administering SUSTIVA to these patients [see Warnings and Precautions (5.8) and Clinical Pharmacology (12.3)].

10 OVERDOSAGE

Some patients accidentally taking 600 mg twice daily have reported increased nervous system symptoms. One patient experienced involuntary muscle contractions.

Treatment of overdose with SUSTIVA should consist of general supportive measures, including monitoring of vital signs and observation of the patient’s clinical status. Administration of activated charcoal may be used to aid removal of unabsorbed drug. There is no specific antidote for overdose with SUSTIVA. Since efavirenz is highly protein bound, dialysis is unlikely to significantly remove the drug from blood.

11 DESCRIPTION

SUSTIVA® (efavirenz) is an HIV-1 specific, non-nucleoside, reverse transcriptase inhibitor (NNRTI). Efavirenz is chemically described as (S)-6-chloro-4-(cyclopropylethynyl)-1,4-dihydro-4-(trifluoromethyl)-2H-3,1-benzoxazin-2-one. Its empirical formula is C14H9ClF3NO2 and its structural formula is:

Efavirenz is a white to slightly pink crystalline powder with a molecular mass of 315.68. It is practically insoluble in water (<10 microgram/mL).

Capsules: SUSTIVA is available as capsules for oral administration containing either 50 mg or 200 mg of efavirenz and the following inactive ingredients: lactose monohydrate, magnesium stearate, sodium lauryl sulfate, and sodium starch glycolate. The capsule shell contains the following inactive ingredients and dyes: gelatin, sodium lauryl sulfate, titanium dioxide, and/or yellow iron oxide. The capsule shells may also contain silicon dioxide. The capsules are printed with ink containing carmine 40 blue, FD&C Blue No. 2, and titanium dioxide.

Tablets: SUSTIVA is available as film-coated tablets for oral administration containing 600 mg of efavirenz and the following inactive ingredients: croscarmellose sodium, hydroxypropyl cellulose, lactose monohydrate, magnesium stearate, microcrystalline cellulose, and sodium lauryl sulfate. The film coating contains Opadry Yellow and Opadry Clear. The tablets are polished with carnauba wax and printed with purple ink, Opacode WB.

12 CLINICAL PHARMACOLOGY

12.1 Mechanism of Action

Efavirenz is an antiviral drug [see Clinical Pharmacology (12.4)].

12.3 Pharmacokinetics

Absorption

Peak efavirenz plasma concentrations of 1.6-9.1 μM were attained by 5 hours following single oral doses of 100 mg to 1600 mg administered to uninfected volunteers. Dose-related increases in Cmax and AUC were seen for doses up to 1600 mg; the increases were less than proportional suggesting diminished absorption at higher doses.

In HIV-1-infected patients at steady state, mean Cmax, mean Cmin, and mean AUC were dose proportional following 200-mg, 400-mg, and 600-mg daily doses. Time-to-peak plasma concentrations were approximately 3-5 hours and steady-state plasma concentrations were reached in 6-10 days. In 35 patients receiving SUSTIVA 600 mg once daily, steady-state Cmax was 12.9 ± 3.7 μM (mean ± SD), steady-state Cmin was 5.6 ± 3.2 μM, and AUC was 184 ± 73 μM•h.

Effect of Food on Oral Absorption:

Capsules: Administration of a single 600-mg dose of efavirenz capsules with a high-fat/high-caloric meal (894 kcal, 54 g fat, 54% calories from fat) or a reduced-fat/normal-caloric meal (440 kcal, 2 g fat, 4% calories from fat) was associated with a mean increase of 22% and 17% in efavirenz AUC∞ and a mean increase of 39% and 51% in efavirenz Cmax, respectively, relative to the exposures achieved when given under fasted conditions. See Dosage and Administration (2) and Patient Counseling Information (17.3).

Tablets: Administration of a single 600-mg efavirenz tablet with a high-fat/high-caloric meal (approximately 1000 kcal, 500-600 kcal from fat) was associated with a 28% increase in mean AUC∞ of efavirenz and a 79% increase in mean Cmax of efavirenz relative to the exposures achieved under fasted conditions. See Dosage and Administration (2) and Patient Counseling Information (17.3).

Distribution

Efavirenz is highly bound (approximately 99.5-99.75%) to human plasma proteins, predominantly albumin. In HIV-1 infected patients (n=9) who received SUSTIVA 200 to 600 mg once daily for at least one month, cerebrospinal fluid concentrations ranged from 0.26 to 1.19% (mean 0.69%) of the corresponding plasma concentration. This proportion is approximately 3-fold higher than the non-protein-bound (free) fraction of efavirenz in plasma.

Metabolism

Studies in humans and in vitro studies using human liver microsomes have demonstrated that efavirenz is principally metabolized by the cytochrome P450 system to hydroxylated metabolites with subsequent glucuronidation of these hydroxylated metabolites. These metabolites are essentially inactive against HIV-1. The in vitro studies suggest that CYP3A and CYP2B6 are the major isozymes responsible for efavirenz metabolism.

Efavirenz has been shown to induce CYP enzymes, resulting in the induction of its own metabolism. Multiple doses of 200-400 mg per day for 10 days resulted in a lower than predicted extent of accumulation (22-42% lower) and a shorter terminal half-life of 40-55 hours (single dose half-life 52-76 hours).

Elimination

Efavirenz has a terminal half-life of 52-76 hours after single doses and 40-55 hours after multiple doses. A one-month mass balance/excretion study was conducted using 400 mg per day with a ^14C-labeled dose administered on Day 8. Approximately 14-34% of the radiolabel was recovered in the urine and 16-61% was recovered in the feces. Nearly all of the urinary excretion of the radiolabeled drug was in the form of metabolites. Efavirenz accounted for the majority of the total radioactivity measured in feces.

Special Populations

Gender and race: The pharmacokinetics of efavirenz in patients appear to be similar between men and women and among the racial groups studied.

Renal impairment: The pharmacokinetics of efavirenz have not been studied in patients with renal insufficiency; however, less than 1% of efavirenz is excreted unchanged in the urine, so the impact of renal impairment on efavirenz elimination should be minimal.

Hepatic impairment: A multiple-dose study showed no significant effect on efavirenz pharmacokinetics in patients with mild hepatic impairment (Child-Pugh Class A) compared with controls. There were insufficient data to determine whether moderate or severe hepatic impairment (Child-Pugh Class B or C) affects efavirenz pharmacokinetics.

Drug Interaction Studies

Efavirenz has been shown in vivo to cause hepatic enzyme induction, thus increasing the biotransformation of some drugs metabolized by CYP3A and CYP2B6. In vitro studies have shown that efavirenz inhibited CYP isozymes 2C9, 2C19, and 3A4 with Ki values (8.5-17 μM) in the range of observed efavirenz plasma concentrations. In in vitro studies, efavirenz did not inhibit CYP2E1 and inhibited CYP2D6 and CYP1A2 (Ki values 82-160 μM) only at concentrations well above those achieved clinically. The inhibitory effect on CYP3A is expected to be similar between 200-mg, 400-mg, and 600-mg doses of efavirenz. Coadministration of efavirenz with drugs primarily metabolized by 2C9, 2C19, and 3A isozymes may result in altered plasma concentrations of the coadministered drug. Drugs which induce CYP3A activity would be expected to increase the clearance of efavirenz resulting in lowered plasma concentrations.

Drug interaction studies were performed with efavirenz and other drugs likely to be coadministered or drugs commonly used as probes for pharmacokinetic interaction. The effects of coadministration of efavirenz on the Cmax, AUC, and Cmin are summarized in Table 8 (effect of efavirenz on other drugs) and Table 9 (effect of other drugs on efavirenz). For information regarding clinical recommendations see Contraindications (4.2) and Drug Interactions (7.1).

Table 8: Effect of Efavirenz on Coadministered Drug Plasma Cmax, AUC, and Cmin
Coadministered Drug | Dose | Efavirenz Dose | Number of Subjects | Coadministered Drug (mean % change)
Coadministered Drug | Dose | Efavirenz Dose | Number of Subjects | Cmax (90% CI) | AUC (90% CI) | Cmin (90% CI)
Atazanavir | 400 mg qd with a light meal d 1‑20 | 600 mg qd with a light meal d 7‑20 | 27 | ↓ 59% (49-67%) | ↓ 74% (68-78%) | ↓ 93% (90-95%)
 | 400 mg qd d 1‑6, then 300 mg qd d 7‑20 with ritonavir 100 mg qd and a light meal | 600 mg qd 2 h after atazanavir and ritonavir d 7‑20 | 13 | ↑ 14%a (↓ 17-↑ 58%) | ↑ 39%a (2-88%) | ↑ 48%a (24-76%)
 | 300 mg qd/ritonavir 100 mg qd d 1‑10 (pm), then 400 mg qd/ritonavir 100 mg qd d 11‑24 (pm) (simultaneous with efavirenz) | 600 mg qd with a light snack d 11‑24 (pm) | 14 | ↑ 17% (8-27%) | ↔ | ↓ 42% (31-51%)
Indinavir | 1000 mg q8h x 10 days | 600 mg qd x 10 days | 20
 | After morning dose |  |  | ↔b | ↓ 33%b (26-39%) | ↓ 39%b (24-51%)
 | After afternoon dose |  |  | ↔b | ↓ 37%b (26-46%) | ↓ 52%b (47-57%)
 | After evening dose |  |  | ↓ 29%b (11-43%) | ↓ 46%b (37-54%) | ↓ 57%b (50-63%)
Lopinavir/ ritonavir | 400/100 mg capsule q12h x 9 days | 600 mg qd x 9 days | 11,7c | ↔d | ↓ 19%d (↓ 36-↑ 3%) | ↓ 39%d (3-62%)
 | 600/150 mg tablet q12h x 10 days with efavirenz compared to 400/100 mg q12h alone | 600 mg qd x 9 days | 23 | ↑ 36%d (28-44%) | ↑ 36%d (28-44%) | ↑ 32%d (21-44%)
Nelfinavir | 750 mg q8h x 7 days | 600 mg qd x 7 days | 10 | ↑ 21% (10-33%) | ↑ 20% (8-34%) | ↔
Metabolite AG-1402 |  |  |  | ↓ 40% (30-48%) | ↓ 37% (25-48%) | ↓ 43% (21-59%)
Ritonavir | 500 mg q12h x 8 days | 600 mg qd x 10 days | 11
 | After AM dose |  |  | ↑ 24% (12-38%) | ↑ 18% (6-33%) | ↑ 42% (9-86%)e
 | After PM dose |  |  | ↔ | ↔ | ↑ 24% (3-50%)e
Saquinavir SGCf | 1200 mg q8h x 10 days | 600 mg qd x 10 days | 12 | ↓ 50% (28-66%) | ↓ 62% (45-74%) | ↓ 56% (16-77%)e
Lamivudine | 150 mg q12h x 14 days | 600 mg qd x 14 days | 9 | ↔ | ↔ | ↑ 265% (37-873%)
Tenofovirg | 300 mg qd | 600 mg qd x 14 days | 29 | ↔ | ↔ | ↔
Zidovudine | 300 mg q12h x 14 days | 600 mg qd x 14 days | 9 | ↔ | ↔ | ↑ 225% (43-640%)
Maraviroc | 100 mg bid | 600 mg qd | 12 | ↓ 51% (37-62%) | ↓ 45% (38-51%) | ↓ 45% (28-57%)
Raltegravir | 400 mg single dose | 600 mg qd | 9 | ↓ 36% (2-59%) | ↓ 36% (20-48%) | ↓ 21% (↓ 51-↑ 28%)
Boceprevir | 800 mg tid x 6 days | 600 mg qd x 16 days | NA | ↓ 8% (↓ 22-↑ 8%) | ↓ 19% (11-25%) | ↓ 44% (26-58%)
Telaprevir | 750 mg q8h x 10 days | 600 mg qd x 20 days | 21 | ↓ 9% (↓ 18-↑ 2%) | ↓ 26% (16-35%) | ↓ 47% (35-56%)
Azithromycin | 600 mg single dose | 400 mg qd x 7 days | 14 | ↑ 22% (4-42%) | ↔ | NA
Clarithromycin | 500 mg q12h x 7 days | 400 mg qd x 7 days | 11 | ↓ 26% (15-35%) | ↓ 39% (30-46%) | ↓ 53% (42-63%)
14-OH metabolite |  |  |  | ↑ 49% (32-69%) | ↑ 34% (18-53%) | ↑ 26% (9-45%)
Fluconazole | 200 mg x 7 days | 400 mg qd x 7 days | 10 | ↔ | ↔ | ↔
Itraconazole | 200 mg q12h x 28 days | 600 mg qd x 14 days | 18 | ↓ 37% (20-51%) | ↓ 39% (21-53%) | ↓ 44% (27-58%)
Hydroxy-itraconazole |  |  |  | ↓ 35% (12-52%) | ↓ 37% (14-55%) | ↓ 43% (18-60%)
Posaconazole | 400 mg (oral suspension) bid x 10 and 20 days | 400 mg qd x 10 and 20 days | 11 | ↓ 45% (34-53%) | ↓ 50% (40-57%) | NA
Rifabutin | 300 mg qd x 14 days | 600 mg qd x 14 days | 9 | ↓ 32% (15-46%) | ↓ 38% (28-47%) | ↓ 45% (31-56%)
Voriconazole | 400 mg po q12h x 1 day, then 200 mg po q12h x 8 days | 400 mg qd x 9 days | NA | ↓ 61%h | ↓ 77%h | NA
 | 300 mg po q12h days 2‑7 | 300 mg qd x 7 days | NA | ↓ 36%i (21-49%) | ↓ 55%i (45-62%) | NA
 | 400 mg po q12h days 2‑7 | 300 mg qd x 7 days | NA | ↑ 23%i (↓ 1-↑ 53%) | ↓ 7%i (↓ 23-↑ 13%) | NA
Atorvastatin | 10 mg qd x 4 days | 600 mg qd x 15 days | 14 | ↓ 14% (1-26%) | ↓ 43% (34-50%) | ↓ 69% (49-81%)
Total active (including metabolites) |  |  |  | ↓ 15% (2-26%) | ↓ 32% (21-41%) | ↓ 48% (23-64%)
Pravastatin | 40 mg qd x 4 days | 600 mg qd x 15 days | 13 | ↓ 32% (↓ 59-↑ 12%) | ↓ 44% (26-57%) | ↓ 19% (0-35%)
Simvastatin | 40 mg qd x 4 days | 600 mg qd x 15 days | 14 | ↓ 72% (63-79%) | ↓ 68% (62-73%) | ↓ 45% (20-62%)
Total active (including metabolites) |  |  |  | ↓ 68% (55-78%) | ↓ 60% (52-68%) | NAj
Carbamazepine | 200 mg qd x 3 days, 200 mg bid x 3 days, then 400 mg qd x 29 days | 600 mg qd x 14 days | 12 | ↓ 20% (15-24%) | ↓ 27% (20-33%) | ↓ 35% (24-44%)
Epoxide metabolite |  |  |  | ↔ | ↔ | ↓ 13% (↓ 30-↑ 7%)
Cetirizine | 10 mg single dose | 600 mg qd x 10 days | 11 | ↓ 24% (18-30%) | ↔ | NA
Diltiazem | 240 mg x 21 days | 600 mg qd x 14 days | 13 | ↓ 60% (50-68%) | ↓ 69% (55-79%) | ↓ 63% (44-75%)
Desacetyl diltiazem |  |  |  | ↓ 64% (57-69%) | ↓ 75% (59-84%) | ↓ 62% (44-75%)
N- monodesmethyl diltiazem |  |  |  | ↓ 28% (7-44%) | ↓ 37% (17-52%) | ↓ 37% (17-52%)
Ethinyl estradiol/ Norgestimate | 0.035 mg/ 0.25 mg x 14 days | 600 mg qd x 14 days
Ethinyl estradiol |  |  | 21 | ↔ | ↔ | ↔
Norelgestromin |  |  | 21 | ↓ 46% (39-52%) | ↓ 64% (62-67%) | ↓ 82% (79-85%)
Levonorgestrel |  |  | 6 | ↓ 80% (77-83%) | ↓ 83% (79-87%) | ↓ 86% (80-90%)
Lorazepam | 2 mg single dose | 600 mg qd x 10 days | 12 | ↑ 16% (2-32%) | ↔ | NA
Methadone | Stable maintenance 35- 100 mg daily | 600 mg qd x 14-21 days | 11 | ↓ 45% (25-59%) | ↓ 52% (33-66%) | NA
Bupropion | 150 mg single dose (sustained-release) | 600 mg qd x 14 days | 13 | ↓ 34% (21-47%) | ↓ 55% (48-62%) | NA
Hydroxy- bupropion |  |  |  | ↑ 50% (20-80%) | ↔ | NA
Paroxetine | 20 mg qd x 14 days | 600 mg qd x 14 days | 16 | ↔ | ↔ | ↔
Sertraline | 50 mg qd x 14 days | 600 mg qd x 14 days | 13 | ↓ 29% (15-40%) | ↓ 39% (27-50%) | ↓ 46% (31-58%)
↑ Indicates increase ↓ Indicates decrease ↔ Indicates no change or a mean increase or decrease of <10%.
a Compared with atazanavir 400 mg qd alone.
b Comparator dose of indinavir was 800 mg q8h x 10 days.
c Parallel-group design; n for efavirenz + lopinavir/ritonavir, n for lopinavir/ritonavir alone.
d Values are for lopinavir; the pharmacokinetics of ritonavir in this study were unaffected by concurrent efavirenz.
e 95% CI.
f Soft Gelatin Capsule.
g Tenofovir disoproxil fumarate.
h 90% CI not available.
i Relative to steady-state administration of voriconazole (400 mg for 1 day, then 200 mg po q12h for 2 days).
j Not available because of insufficient data.
NA = not available.

Table 9: Effect of Coadministered Drug on Efavirenz Plasma Cmax, AUC, and Cmin
 |  |  |  | Efavirenz (mean % change)
Coadministered Drug | Dose | Efavirenz Dose | Number of Subjects | Cmax (90% CI) | AUC (90% CI) | Cmin (90% CI)
Indinavir | 800 mg q8h x 14 days | 200 mg qd x 14 days | 11 | ↔ | ↔ | ↔
Lopinavir/ ritonavir | 400/100 mg q12h x 9 days | 600 mg qd x 9 days | 11,12a | ↔ | ↓ 16% (↓ 38-↑ 15%) | ↓ 16% (↓ 42-↑ 20%)
Nelfinavir | 750 mg q8h x 7 days | 600 mg qd x 7 days | 10 | ↓ 12% (↓ 32-↑ 13%)b | ↓ 12% (↓ 35-↑ 18%)b | ↓ 21% (↓ 53-↑ 33%)
Ritonavir | 500 mg q12h x 8 days | 600 mg qd x 10 days | 9 | ↑ 14% (4-26%) | ↑ 21% (10-34%) | ↑ 25% (7-46%)b
Saquinavir SGCc | 1200 mg q8h x 10 days | 600 mg qd x 10 days | 13 | ↓ 13% (5-20%) | ↓ 12% (4-19%) | ↓ 14% (2-24%)b
Tenofovird | 300 mg qd | 600 mg qd x 14 days | 30 | ↔ | ↔ | ↔
Boceprevir | 800 mg tid x 6 days | 600 mg qd x 16 days | NA | ↑ 11% (2-20%) | ↑ 20% (15-26%) | NA
Telaprevir | 750 mg q8h x 10 days | 600 mg qd x 20 days | 21 | ↓ 16% (7-24%) | ↓ 7% (2-13%) | ↓ 2% (↓ 6-↑ 2%)
Telaprevir, coadministered with tenofovir disoproxil fumarate (TDF) | 1125 mg q8h x 7 days | 600 mg efavirenz/300 mg TDF qd x 7 days | 15 | ↓ 24% (15-32%) | ↓ 18% (10-26%) | ↓ 10% (↓ 19-↑ 1%)
Telaprevir, coadministered with tenofovir disoproxil fumarate (TDF) | 1500 mg q12h x 7 days | 600 mg efavirenz/300 mg TDF qd x 7 days | 16 | ↓ 20% (14-26%) | ↓ 15% (9-21%) | ↓ 11% (4-18%)
Azithromycin | 600 mg single dose | 400 mg qd x 7 days | 14 | ↔ | ↔ | ↔
Clarithromycin | 500 mg q12h x 7 days | 400 mg qd x 7 days | 12 | ↑ 11% (3-19%) | ↔ | ↔
Fluconazole | 200 mg x 7 days | 400 mg qd x 7 days | 10 | ↔ | ↑ 16% (6-26%) | ↑ 22% (5-41%)
Itraconazole | 200 mg q12h x 14 days | 600 mg qd x 28 days | 16 | ↔ | ↔ | ↔
Rifabutin | 300 mg qd x 14 days | 600 mg qd x 14 days | 11 | ↔ | ↔ | ↓ 12% (↓ 24-↑ 1%)
Rifampin | 600 mg x 7 days | 600 mg qd x 7 days | 12 | ↓ 20% (11-28%) | ↓ 26% (15-36%) | ↓ 32% (15-46%)
Voriconazole | 400 mg po q12h x 1 day, then 200 mg po q12h x 8 days | 400 mg qd x 9 days | NA | ↑ 38%e | ↑ 44%e | NA
 | 300 mg po q12h days 2-7 | 300 mg qd x 7 days | NA | ↓ 14%f (7-21%) | ↔f | NA
 | 400 mg po q12h days 2-7 | 300 mg qd x 7 days | NA | ↔f | ↑ 17%f (6-29%) | NA
Atorvastatin | 10 mg qd x 4 days | 600 mg qd x 15 days | 14 | ↔ | ↔ | ↔
Pravastatin | 40 mg qd x 4 days | 600 mg qd x 15 days | 11 | ↔ | ↔ | ↔
Simvastatin | 40 mg qd x 4 days | 600 mg qd x 15 days | 14 | ↓ 12% (↓ 28-↑ 8%) | ↔ | ↓ 12% (↓ 25-↑ 3%)
Aluminum hydroxide 400 mg, magnesium hydroxide 400 mg, plus simethicone 40 mg | 30 mL single dose | 400 mg single dose | 17 | ↔ | ↔ | NA
Carbamazepine | 200 mg qd x 3 days, 200 mg bid x 3 days, then 400 mg qd x 15 days | 600 mg qd x 35 days | 14 | ↓ 21% (15-26%) | ↓ 36% (32-40%) | ↓ 47% (41-53%)
Cetirizine | 10 mg single dose | 600 mg qd x 10 days | 11 | ↔ | ↔ | ↔
Diltiazem | 240 mg x 14 days | 600 mg qd x 28 days | 12 | ↑ 16% (6-26%) | ↑ 11% (5-18%) | ↑ 13% (1-26%)
Famotidine | 40 mg single dose | 400 mg single dose | 17 | ↔ | ↔ | NA
Paroxetine | 20 mg qd x 14 days | 600 mg qd x 14 days | 12 | ↔ | ↔ | ↔
Sertraline | 50 mg qd x 14 days | 600 mg qd x 14 days | 13 | ↑ 11% (6-16%) | ↔ | ↔
↑ Indicates increase ↓ Indicates decrease ↔ Indicates no change or a mean increase or decrease of <10%.
a Parallel-group design; n for efavirenz + lopinavir/ritonavir, n for efavirenz alone.
b 95% CI.
c Soft Gelatin Capsule.
d Tenofovir disoproxil fumarate.
e 90% CI not available.
f Relative to steady-state administration of efavirenz (600 mg once daily for 9 days).
NA = not available.

12.4 Microbiology

Mechanism of Action

Efavirenz (EFV) is an NNRTI of HIV-1. EFV activity is mediated predominantly by noncompetitive inhibition of HIV-1 reverse transcriptase (RT). HIV-2 RT and human cellular DNA polymerases α, β, γ, and δ are not inhibited by EFV.

Antiviral Activity in Cell Culture

The concentration of EFV inhibiting replication of wild-type laboratory adapted strains and clinical isolates in cell culture by 90-95% (EC90-95) ranged from 1.7 to 25 nM in lymphoblastoid cell lines, peripheral blood mononuclear cells (PBMCs), and macrophage/monocyte cultures. EFV demonstrated antiviral activity against clade B and most non-clade B isolates (subtypes A, AE, AG, C, D, F, G, J, N), but had reduced antiviral activity against group O viruses. EFV demonstrated additive antiviral activity without cytotoxicity against HIV-1 in cell culture when combined with the NNRTIs delavirdine (DLV) and nevirapine (NVP), NRTIs (abacavir, didanosine, emtricitabine, lamivudine [LAM], stavudine, tenofovir, zalcitabine, zidovudine [ZDV]), PIs (amprenavir, indinavir [IDV], lopinavir, nelfinavir, ritonavir, saquinavir), and the fusion inhibitor enfuvirtide. EFV demonstrated additive to antagonistic antiviral activity in cell culture with atazanavir. EFV was not antagonistic with adefovir, used for the treatment of hepatitis B virus infection, or ribavirin, used in combination with interferon for the treatment of hepatitis C virus infection.

Resistance

In cell culture, HIV-1 isolates with reduced susceptibility to EFV (>380-fold increase in EC90 value) emerged rapidly in the presence of drug. Genotypic characterization of these viruses identified single amino acid substitutions L100I or V179D, double substitutions L100I/V108I, and triple substitutions L100I/V179D/Y181C in RT.

Clinical studies

Clinical isolates with reduced susceptibility in cell culture to EFV have been obtained. One or more RT substitutions at amino acid positions 98, 100, 101, 103, 106, 108, 188, 190, 225, and 227 were observed in patients failing treatment with EFV in combination with IDV, or with ZDV plus LAM. The mutation K103N was the most frequently observed. Long-term resistance surveillance (average 52 weeks, range 4-106 weeks) analyzed 28 matching baseline and virologic failure isolates. Sixty-one percent (17/28) of these failure isolates had decreased EFV susceptibility in cell culture with a median 88-fold change in EFV susceptibility (EC50 value) from reference. The most frequent NNRTI substitution to develop in these patient isolates was K103N (54%). Other NNRTI substitutions that developed included L100I (7%), K101E/Q/R (14%), V108I (11%), G190S/T/A (7%), P225H (18%), and M230I/L (11%).

Cross-Resistance

Cross-resistance among NNRTIs has been observed. Clinical isolates previously characterized as EFV-resistant were also phenotypically resistant in cell culture to DLV and NVP compared to baseline. DLV- and/or NVP-resistant clinical viral isolates with NNRTI resistance-associated substitutions (A98G, L100I, K101E/P, K103N/S, V106A, Y181X, Y188X, G190X, P225H, F227L, or M230L) showed reduced susceptibility to EFV in cell culture. Greater than 90% of NRTI-resistant clinical isolates tested in cell culture retained susceptibility to EFV.

13 NONCLINICAL TOXICOLOGY

13.1 Carcinogenesis, Mutagenesis, Impairment of Fertility

Carcinogenesis

Long-term carcinogenicity studies in mice and rats were carried out with efavirenz. Mice were dosed with 0, 25, 75, 150, or 300 mg/kg/day for 2 years. Incidences of hepatocellular adenomas and carcinomas and pulmonary alveolar/bronchiolar adenomas were increased above background in females. No increases in tumor incidence above background were seen in males. There was no NOAEL in females established for this study because tumor findings occurred at all doses. AUC at the NOAEL (150 mg/kg) in the males was approximately 0.9 times that in humans at the recommended clinical dose. In the rat study, no increases in tumor incidence were observed at doses up to 100 mg/kg/day, for which AUCs were 0.1 (males) or 0.2 (females) times those in humans at the recommended clinical dose.

Mutagenesis

Efavirenz tested negative in a battery of in vitro and in vivo genotoxicity assays. These included bacterial mutation assays in S. typhimurium and E. coli, mammalian mutation assays in Chinese hamster ovary cells, chromosome aberration assays in human peripheral blood lymphocytes or Chinese hamster ovary cells, and an in vivo mouse bone marrow micronucleus assay.

Impairment of Fertility

Efavirenz did not impair mating or fertility of male or female rats, and did not affect sperm of treated male rats. The reproductive performance of offspring born to female rats given efavirenz was not affected. The AUCs at the NOAEL values in male (200 mg/kg) and female (100 mg/kg) rats were approximately ≤0.15 times that in humans at the recommended clinical dose.

13.2 Animal Toxicology

Nonsustained convulsions were observed in 6 of 20 monkeys receiving efavirenz at doses yielding plasma AUC values 4- to 13-fold greater than those in humans given the recommended dose [see Warnings and Precautions (5.9)].

14 CLINICAL STUDIES

Study 006, a randomized, open-label trial, compared SUSTIVA (600 mg once daily) + zidovudine (ZDV, 300 mg q12h) + lamivudine (LAM, 150 mg q12h) or SUSTIVA (600 mg once daily) + indinavir (IDV, 1000 mg q8h) with indinavir (800 mg q8h) + zidovudine (300 mg q12h) + lamivudine (150 mg q12h). Twelve hundred sixty-six patients (mean age 36.5 years [range 18-81], 60% Caucasian, 83% male) were enrolled. All patients were efavirenz-, lamivudine-, NNRTI-, and PI-naive at study entry. The median baseline CD4+ cell count was 320 cells/mm^3 and the median baseline HIV-1 RNA level was 4.8 log10 copies/mL. Treatment outcomes with standard assay (assay limit 400 copies/mL) through 48 and 168 weeks are shown in Table 10. Plasma HIV RNA levels were quantified with standard (assay limit 400 copies/mL) and ultrasensitive (assay limit 50 copies/mL) versions of the AMPLICOR HIV-1 MONITOR assay. During the study, version 1.5 of the assay was introduced in Europe to enhance detection of non-clade B virus.

Table 10: Outcomes of Randomized Treatment Through 48 and 168 Weeks, Study 006
 | SUSTIVA + ZDV + LAM (n=422) |  | SUSTIVA + IDV (n=429) |  | IDV + ZDV + LAM (n=415)
Outcome | Week 48 | Week 168 | Week 48 | Week 168 | Week 48 | Week 168
Respondera | 69% | 48% | 57% | 40% | 50% | 29%
Virologic failureb | 6% | 12% | 15% | 20% | 13% | 19%
Discontinued for adverse events | 7% | 8% | 6% | 8% | 16% | 20%
Discontinued for other reasonsc | 17% | 31% | 22% | 32% | 21% | 32%
CD4+ cell count (cells/mm^3)
Observed subjects (n) | (279) | (205) | (256) | (158) | (228) | (129)
Mean change from baseline | 190 | 329 | 191 | 319 | 180 | 329
a Patients achieved and maintained confirmed HIV-1 RNA <400 copies/mL through Week 48 or Week 168.
b Includes patients who rebounded, patients who were on study at Week 48 and failed to achieve confirmed HIV-1 RNA <400 copies/mL at time of discontinuation, and patients who discontinued due to lack of efficacy.
c Includes consent withdrawn, lost to follow-up, noncompliance, never treated, missing data, protocol violation, death, and other reasons. Patients with HIV-1 RNA levels <400 copies/mL who chose not to continue in the voluntary extension phases of the study were censored at date of last dose of study medication.

For patients treated with SUSTIVA + zidovudine + lamivudine, SUSTIVA + indinavir, or indinavir + zidovudine + lamivudine, the percentage of responders with HIV-1 RNA <50 copies/mL was 65%, 50%, and 45%, respectively, through 48 weeks, and 43%, 31%, and 23%, respectively, through 168 weeks. A Kaplan-Meier analysis of time to loss of virologic response (HIV RNA <400 copies/mL) suggests that both the trends of virologic response and differences in response continue through 4 years.

ACTG 364 is a randomized, double-blind, placebo-controlled, 48-week study in NRTI-experienced patients who had completed two prior ACTG studies. One-hundred ninety-six patients (mean age 41 years [range 18-76], 74% Caucasian, 88% male) received NRTIs in combination with SUSTIVA (efavirenz) (600 mg once daily), or nelfinavir (NFV, 750 mg three times daily), or SUSTIVA (600 mg once daily) + nelfinavir in a randomized, double-blinded manner. The mean baseline CD4+ cell count was 389 cells/mm^3 and mean baseline HIV-1 RNA level was 8130 copies/mL. Upon entry into the study, all patients were assigned a new open-label NRTI regimen, which was dependent on their previous NRTI treatment experience. There was no significant difference in the mean CD4+ cell count among treatment groups; the overall mean increase was approximately 100 cells at 48 weeks among patients who continued on study regimens. Treatment outcomes are shown in Table 11. Plasma HIV RNA levels were quantified with the AMPLICOR HIV-1 MONITOR assay using a lower limit of quantification of 500 copies/mL.

Table 11: Outcomes of Randomized Treatment Through 48 Weeks, Study ACTG 364*
Outcome | SUSTIVA + NFV + NRTIs (n=65) | SUSTIVA + NRTIs (n=65) | NFV + NRTIs (n=66)
HIV-1 RNA <500 copies/mLa | 71% | 63% | 41%
HIV-1 RNA ≥500 copies/mLb | 17% | 34% | 54%
CDC Category C Event | 2% | 0% | 0%
Discontinuations for adverse eventsc | 3% | 3% | 5%
Discontinuations for other reasonsd | 8% | 0% | 0%
* For some patients, Week 56 data were used to confirm the status at Week 48.
a Subjects achieved virologic response (two consecutive viral loads <500 copies/mL) and maintained it through Week 48.
b Includes viral rebound and failure to achieve confirmed <500 copies/mL by Week 48.
c See Adverse Reactions (6.1) for a safety profile of these regimens.
d Includes loss to follow-up, consent withdrawn, noncompliance.

A Kaplan-Meier analysis of time to treatment failure through 72 weeks demonstrates a longer duration of virologic suppression (HIV RNA <500 copies/mL) in the SUSTIVA-containing treatment arms.

16 HOW SUPPLIED/STORAGE AND HANDLING

16.1 Capsules

SUSTIVA® (efavirenz) capsules are available as follows:

Capsules 200 mg are gold color, reverse printed with “SUSTIVA” on the body and imprinted “200 mg” on the cap.

Capsules 50 mg are gold color and white, printed with “SUSTIVA” on the gold color cap and reverse printed “50 mg” on the white body.

16.2 Tablets

SUSTIVA® (efavirenz) tablets are available as follows:

Tablets 600 mg are yellow, capsular-shaped, film-coated tablets, with “SUSTIVA” printed on both sides.

Bottles of 30 NDC 54868-4668-0

16.3 Storage

SUSTIVA capsules and SUSTIVA tablets should be stored at 25° C (77° F); excursions permitted to 15°–30° C (59°–86° F) [see USP Controlled Room Temperature].

17 PATIENT COUNSELING INFORMATION

See FDA-approved patient labeling (Patient Information).

17.1 Drug Interactions

A statement to patients and healthcare providers is included on the product’s bottle labels:
ALERT: Find out about medicines that should NOT be taken with SUSTIVA.

SUSTIVA may interact with some drugs; therefore, patients should be advised to report to their doctor the use of any other prescription, nonprescription medication, or herbal products, particularly St. John’s wort.

17.2 General Information for Patients

Patients should be informed that SUSTIVA is not a cure for HIV-1 infection and patients may continue to experience illnesses associated with HIV-1 infection, including opportunistic infections. Patients should remain under the care of a physician while taking SUSTIVA.

Patients should be advised to avoid doing things that can spread HIV-1 infection to others.

- Do not share needles or other injection equipment.
- Do not share personal items that can have blood or body fluids on them, like toothbrushes and razor blades.
- Do not have any kind of sex without protection. Always practice safe sex by using a latex or polyurethane condom to lower the chance of sexual contact with semen, vaginal secretions, or blood.
- Do not breast-feed. It is not known if SUSTIVA can be passed to your baby in your breast milk and whether it could harm your baby. Also, mothers with HIV-1 should not breast-feed because HIV-1 can be passed to the baby in breast milk.

17.3 Dosing Instructions

Patients should be advised to take SUSTIVA every day as prescribed. SUSTIVA must always be used in combination with other antiretroviral drugs. Patients should be advised to take SUSTIVA on an empty stomach, preferably at bedtime. Taking SUSTIVA with food increases efavirenz concentrations and may increase the frequency of adverse reactions. Dosing at bedtime may improve the tolerability of nervous system symptoms [see Dosage and Administration (2) and Adverse Reactions (6.1)].

17.4 Nervous System Symptoms

Patients should be informed that central nervous system symptoms (NSS) including dizziness, insomnia, impaired concentration, drowsiness, and abnormal dreams are commonly reported during the first weeks of therapy with SUSTIVA [see Warnings and Precautions (5.5)]. Dosing at bedtime may improve the tolerability of these symptoms, which are likely to improve with continued therapy. Patients should be alerted to the potential for additive effects when SUSTIVA is used concomitantly with alcohol or psychoactive drugs. Patients should be instructed that if they experience NSS they should avoid potentially hazardous tasks such as driving or operating machinery.

17.5 Psychiatric Symptoms

Patients should be informed that serious psychiatric symptoms including severe depression, suicide attempts, aggressive behavior, delusions, paranoia, and psychosis-like symptoms have been reported in patients receiving SUSTIVA [see Warnings and Precautions (5.4)]. If they experience severe psychiatric adverse experiences they should seek immediate medical evaluation. Patients should be advised to inform their physician of any history of mental illness or substance abuse.

17.6 Rash

Patients should be informed that a common side effect is rash [see Warnings and Precautions (5.7)]. Rashes usually go away without any change in treatment. However, since rash may be serious, patients should be advised to contact their physician promptly if rash occurs.

17.7 Reproductive Risk Potential

Women receiving SUSTIVA should be instructed to avoid pregnancy [see Warnings and Precautions (5.6)]. A reliable form of barrier contraception must always be used in combination with other methods of contraception, including oral or other hormonal contraception. Because of the long half-life of efavirenz, use of adequate contraceptive measures for 12 weeks after discontinuation of SUSTIVA is recommended. Women should be advised to notify their physician if they become pregnant or plan to become pregnant while taking SUSTIVA. If this drug is used during the first trimester of pregnancy, or if the patient becomes pregnant while taking this drug, she should be apprised of the potential harm to the fetus.

17.8 Fat Redistribution

Patients should be informed that redistribution or accumulation of body fat may occur in patients receiving antiretroviral therapy and that the cause and long-term health effects of these conditions are not known [see Warnings and Precautions (5.12)].

Patient Information

SUSTIVA® (sus-TEE-vah)

[efavirenz (eh-FAH-vih-rehnz)]

capsules and tablets

ALERT: Find out about medicines that should NOT be taken with SUSTIVA.

Please also read the section “MEDICINES YOU SHOULD NOT TAKE WITH SUSTIVA.”

Read this information before you start taking SUSTIVA. Read it again each time you refill your prescription, in case there is any new information. This leaflet provides a summary about SUSTIVA and does not include everything there is to know about your medicine. This information is not meant to take the place of talking with your doctor.

What is SUSTIVA?

SUSTIVA is a medicine used in combination with other medicines to help treat infection with Human Immunodeficiency Virus type 1 (HIV-1), the virus that causes AIDS (acquired immune deficiency syndrome). SUSTIVA is a type of anti-HIV drug called a “non-nucleoside reverse transcriptase inhibitor” (NNRTI). NNRTIs are not used in the treatment of Human Immunodeficiency Virus type 2 (HIV-2) infection.

SUSTIVA works by lowering the amount of HIV-1 in the blood (viral load). SUSTIVA must be taken with other anti-HIV medicines. When taken with other anti-HIV medicines, SUSTIVA has been shown to reduce viral load and increase the number of CD4+ cells, a type of immune cell in blood. SUSTIVA may not have these effects in every patient.

SUSTIVA does not cure HIV or AIDS and you may continue to experience illnesses associated with HIV-1 infection, including opportunistic infections. You should remain under the care of a doctor when using SUSTIVA.

Avoid doing things that can spread HIV-1 infection.

- Do not share needles or other injection equipment.
- Do not share personal items that can have blood or body fluids on them, like toothbrushes and razor blades.
- Do not have any kind of sex without protection. Always practice safe sex by using a latex or polyurethane condom to lower the chance of sexual contact with semen, vaginal secretions, or blood.

What are the possible side effects of SUSTIVA?

Serious psychiatric problems. A small number of patients experience severe depression, strange thoughts, or angry behavior while taking SUSTIVA. Some patients have thoughts of suicide and a few have actually committed suicide. These problems tend to occur more often in patients who have had mental illness. Contact your doctor right away if you think you are having these psychiatric symptoms, so your doctor can decide if you should continue to take SUSTIVA (efavirenz).

Common side effects. Many patients have dizziness, trouble sleeping, drowsiness, trouble concentrating, and/or unusual dreams during treatment with SUSTIVA. These side effects may be reduced if you take SUSTIVA at bedtime on an empty stomach. They also tend to go away after you have taken the medicine for a few weeks. If you have these common side effects, such as dizziness, it does not mean that you will also have serious psychiatric problems, such as severe depression, strange thoughts, or angry behavior. Tell your doctor right away if any of these side effects continue or if they bother you. It is possible that these symptoms may be more severe if SUSTIVA is used with alcohol or mood altering (street) drugs.

If you are dizzy, have trouble concentrating, or are drowsy, avoid activities that may be dangerous, such as driving or operating machinery.

Rash is common. Rashes usually go away without any change in treatment. In a small number of patients, rash may be serious. If you develop a rash, call your doctor right away. Rash may be a serious problem in some children. Tell your child’s doctor right away if you notice rash or any other side effects while your child is taking SUSTIVA.

Other common side effects include tiredness, upset stomach, vomiting, and diarrhea. Some patients taking SUSTIVA have experienced increased levels of lipids (cholesterol and triglycerides) in the blood.

Changes in body fat. Changes in body fat develop in some patients taking anti-HIV medicine. These changes may include an increased amount of fat in the upper back and neck (“buffalo hump”), in the breasts, and around the trunk. Loss of fat from the legs, arms, and face may also happen. The cause and long-term health effects of these fat changes are not known.

Liver problems. Some patients taking SUSTIVA have experienced serious liver problems including liver failure resulting in transplantation or death. Most of these serious side effects occurred in patients with a chronic liver disease such as hepatitis infection, but there have also been a few reports in patients without any existing liver disease.

Tell your doctor or healthcare provider if you notice any side effects while taking SUSTIVA.

Contact your doctor before stopping SUSTIVA because of side effects or for any other reason.

This is not a complete list of side effects possible with SUSTIVA. Ask your doctor or pharmacist for a more complete list of side effects of SUSTIVA and all the medicines you will take.

How should I take SUSTIVA?

General Information

- You should take SUSTIVA on an empty stomach, preferably at bedtime.
- Swallow SUSTIVA with water.
- Taking SUSTIVA with food increases the amount of medicine in your body, which may increase the frequency of side effects.
- Taking SUSTIVA at bedtime may make some side effects less bothersome.
- SUSTIVA must be taken in combination with other anti-HIV medicines. If you take only SUSTIVA, the medicine may stop working.
- Do not miss a dose of SUSTIVA. If you forget to take SUSTIVA, take the missed dose right away, unless it is almost time for your next dose. Do not double the next dose. Carry on with your regular dosing schedule. If you need help in planning the best times to take your medicine, ask your doctor or pharmacist.
- Take the exact amount of SUSTIVA your doctor prescribes. Never change the dose on your own. Do not stop this medicine unless your doctor tells you to stop.
- If you believe you took more than the prescribed amount of SUSTIVA, contact your local Poison Control Center or emergency room right away.
- Tell your doctor if you start any new medicine or change how you take old ones. Your doses may need adjustment.
- When your SUSTIVA supply starts to run low, get more from your doctor or pharmacy. This is very important because the amount of virus in your blood may increase if the medicine is stopped for even a short time. The virus may develop resistance to SUSTIVA and become harder to treat.
- Your doctor may want to do blood tests to check for certain side effects while you take SUSTIVA (efavirenz).

Capsules

- The dose of SUSTIVA capsules for adults is 600 mg (three 200-mg capsules, taken together) once a day by mouth. The dose of SUSTIVA for children may be lower (see “Can children take SUSTIVA?”).

Tablets

- The dose of SUSTIVA tablets for adults is 600 mg (one tablet) once a day by mouth.

Can children take SUSTIVA?

Yes, children who are able to swallow capsules can take SUSTIVA. Rash may be a serious problem in some children. Tell your child’s doctor right away if you notice rash or any other side effects while your child is taking SUSTIVA. The dose of SUSTIVA for children may be lower than the dose for adults. Capsules containing lower doses of SUSTIVA are available. Your child’s doctor will determine the right dose based on your child’s weight.

Who should not take SUSTIVA?

Do not take SUSTIVA if you are allergic to the active ingredient, efavirenz, or to any of the inactive ingredients. Your doctor and pharmacist have a list of the inactive ingredients.

What should I avoid while taking SUSTIVA?

- Women should not become pregnant while taking SUSTIVA and for 12 weeks after stopping it. Serious birth defects have been seen in the offspring of animals and women treated with SUSTIVA during pregnancy. It is not known whether SUSTIVA caused these defects. Tell your doctor right away if you are pregnant. Also talk with your doctor if you want to become pregnant.
- Women should not rely only on hormone-based birth control, such as pills, injections, or implants, because SUSTIVA may make these contraceptives ineffective. Women must use a reliable form of barrier contraception, such as a condom or diaphragm, even if they also use other methods of birth control. SUSTIVA may remain in your blood for a time after therapy is stopped. Therefore, you should continue to use contraceptive measures for 12 weeks after you stop taking SUSTIVA.
- Do not breast-feed if you are taking SUSTIVA. It is not known if SUSTIVA can be passed to your baby in your breast milk and whether it could harm your baby. Also, mothers with HIV-1 should not breast-feed because HIV-1 can be passed to the baby in the breast milk. Talk with your doctor if you are breast-feeding. You may need to stop breast-feeding or use a different medicine.
- Taking SUSTIVA with alcohol or other medicines causing similar side effects as SUSTIVA, such as drowsiness, may increase those side effects.
- Do not take any other medicines without checking with your doctor. These medicines include prescription and nonprescription medicines and herbal products, especially St. John’s wort (Hypericum perforatum).

Before using SUSTIVA, tell your doctor if you

- have problems with your liver or have hepatitis. Your doctor may want to do tests to check your liver while you take SUSTIVA or may switch you to another medicine.
- have ever had mental illness or are using drugs or alcohol.
- have ever had seizures or are taking medicine for seizures [for example, Dilantin (phenytoin), Tegretol (carbamazepine), or phenobarbital]. Your doctor may want to switch you to another medicine or check drug levels in your blood from time to time.

What important information should I know about taking other medicines with SUSTIVA?

SUSTIVA may change the effect of other medicines, including ones for HIV, and cause serious side effects. Your doctor may change your other medicines or change their doses. Other medicines, including herbal products, may affect SUSTIVA. For this reason, it is very important to:

- let all your doctors and pharmacists know that you take SUSTIVA.
- tell your doctors and pharmacists about all medicines you take. This includes those you buy over-the-counter and herbal or natural remedies.

Bring all your prescription and nonprescription medicines as well as any herbal remedies that you are taking when you see a doctor, or make a list of their names, how much you take, and how often you take them. This will give your doctor a complete picture of the medicines you use. Then he or she can decide the best approach for your situation.

Taking SUSTIVA with St. John’s wort (Hypericum perforatum), an herbal product sold as a dietary supplement, or products containing St. John’s wort is not recommended. Talk with your doctor if you are taking or are planning to take St. John’s wort. Taking St. John’s wort may decrease SUSTIVA levels and lead to increased viral load and possible resistance to SUSTIVA or cross-resistance to other anti-HIV drugs.

MEDICINES YOU SHOULD NOT TAKE WITH SUSTIVA

The following medicines may cause serious and life-threatening side effects when taken with SUSTIVA. You should not take any of these medicines while taking SUSTIVA:

- Vascor (bepridil)
- Propulsid (cisapride)
- Versed (midazolam)
- Orap (pimozide)
- Halcion (triazolam)
- Ergot medications (for example, Wigraine and Cafergot)

The following medicine should not be taken with SUSTIVA since it contains efavirenz, the active ingredient in SUSTIVA:

- ATRIPLA (efavirenz, emtricitabine, tenofovir disoproxil fumarate)

The following medicines may need to be replaced with another medicine when taken with SUSTIVA:

- Fortovase, Invirase (saquinavir)
- Biaxin (clarithromycin)
- Carbatrol, Tegretol (carbamazepine)
- Noxafil (posaconazole)
- Sporanox (itraconazole)
- REYATAZ (atazanavir sulfate), if this is not the first time you are receiving treatment for your HIV infection
- Victrelis (boceprevir)

The following medicines may require a change in the dose of either SUSTIVA or the other medicine:

- Calcium channel blockers such as Cardizem or Tiazac (diltiazem), Covera HS or Isoptin SR (verapamil), and others.
- The cholesterol-lowering medicines Lipitor (atorvastatin), PRAVACHOL (pravastatin sodium), and Zocor (simvastatin).
- Crixivan (indinavir)
- Kaletra (lopinavir/ritonavir)
- Methadone
- Mycobutin (rifabutin)
- REYATAZ (atazanavir sulfate). If you are taking SUSTIVA and REYATAZ, you should also be taking Norvir (ritonavir).
- Rifadin (rifampin) or the rifampin-containing medicines Rifamate and Rifater.
- Selzentry (maraviroc)
- Vfend (voriconazole) and SUSTIVA must not be taken together at standard doses. Some doses of voriconazole can be taken at the same time as a lower dose of SUSTIVA, but you must check with your doctor first.
- Zoloft (sertraline)
- Wellbutrin, Wellbutrin SR, Wellbutrin XL, or Zyban (bupropion)
- The immunosuppressant medicines cyclosporine (Gengraf, Neoral, Sandimmune, and others), Prograf (tacrolimus), or Rapamune (sirolimus).

These are not all the medicines that may cause problems if you take SUSTIVA. Be sure to tell your doctor about all medicines that you take.

General advice about SUSTIVA:

Medicines are sometimes prescribed for conditions that are not mentioned in patient information leaflets. Do not use SUSTIVA for a condition for which it was not prescribed. Do not give SUSTIVA to other people, even if they have the same symptoms you have. It may harm them.

Keep SUSTIVA at room temperature (77° F) in the bottle given to you by your pharmacist. The temperature can range from 59° to 86° F.

Keep SUSTIVA out of the reach of children.

This leaflet summarizes the most important information about SUSTIVA. If you would like more information, talk with your doctor. You can ask your pharmacist or doctor for the full prescribing information about SUSTIVA, or you can visit the SUSTIVA website at www.sustiva.com or call 1-800-321-1335.

__________________

SUSTIVA is a registered trademark of Bristol-Myers Squibb Pharma Company, ATRIPLA is a trademark of Bristol-Myers Squibb & Gilead Sciences, LLC, PRAVACHOL is a registered trademark of ER Squibb & Sons, LLC, and REYATAZ is a registered trademark of Bristol-Myers Squibb Company. Other brands listed are the trademarks of their respective owners.

Distributed by:

Bristol-Myers Squibb Company
Princeton, NJ 08543 USA

SUSTIVA® (efavirenz) capsules made in India.

© Bristol-Myers Squibb Company 2012

1262274A8
510230013IN09
Rev August 2012

Distributed by:
Physicians Total Care, Inc.
Tulsa, OK 74146

PACKAGE LABEL

NDC 54868-4668-0 30 Tablets

SUSTIVA® Rx only
(efavirenz) tablets

600 mg

Each tablet contains 600 mg of efavirenz.
DOSAGE: For dosage and full prescribing
information, read accompanying package
insert.
Note to pharmacist: Do not cover
ALERT box with pharmacy label.

ALERT: Find out about medicines that
should NOT be taken with SUSTIVA®